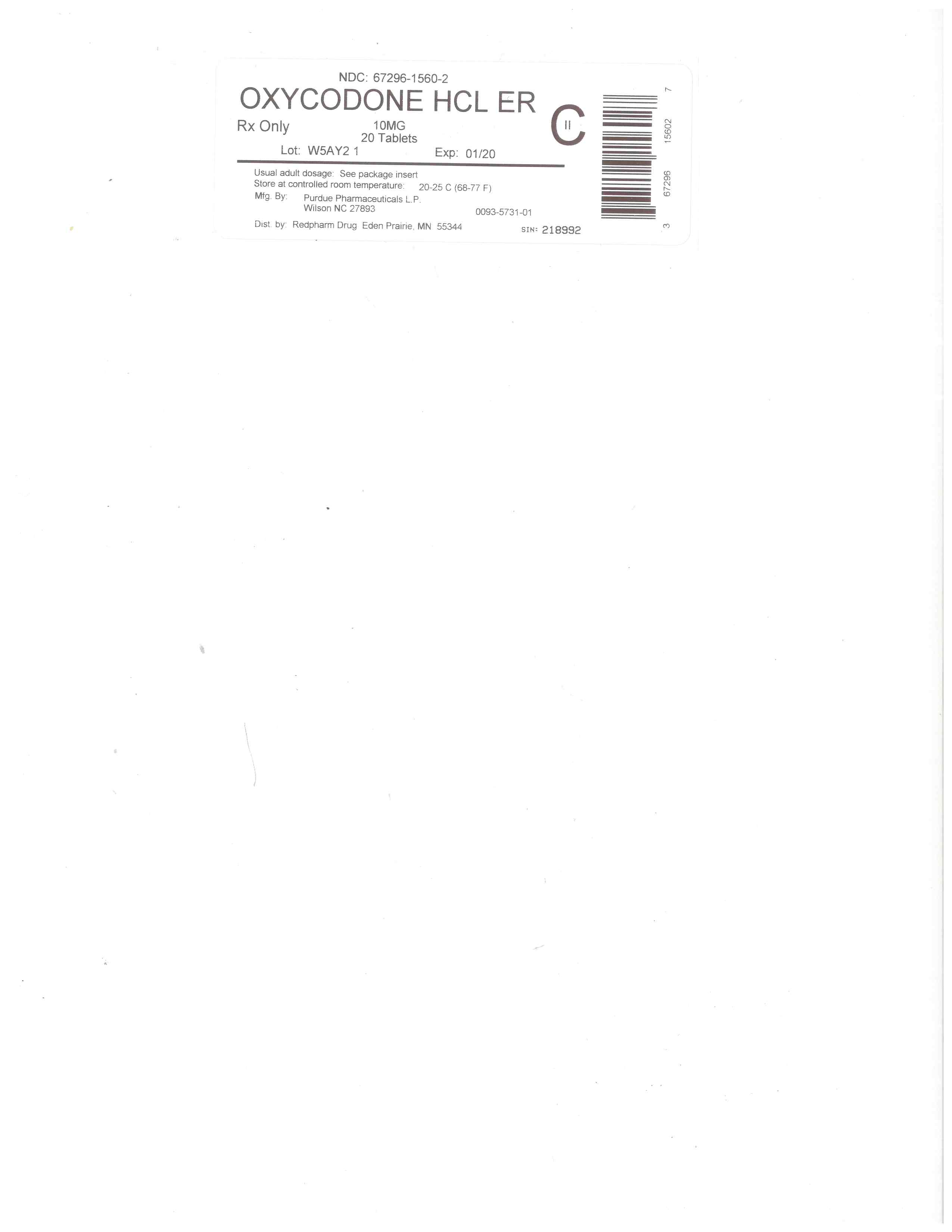 DRUG LABEL: Oxycodone Hydrochloride
NDC: 67296-1560 | Form: TABLET, FILM COATED, EXTENDED RELEASE
Manufacturer: RedPharm Drug, Inc.
Category: prescription | Type: HUMAN PRESCRIPTION DRUG LABEL
Date: 20220121
DEA Schedule: CII

ACTIVE INGREDIENTS: OXYCODONE HYDROCHLORIDE 10 mg/1 1
INACTIVE INGREDIENTS: HYDROXYPROPYL CELLULOSE, UNSPECIFIED; HYPROMELLOSE, UNSPECIFIED; POLYETHYLENE GLYCOL, UNSPECIFIED; MAGNESIUM STEARATE; BUTYLATED HYDROXYTOLUENE; POLYETHYLENE GLYCOL 400; TITANIUM DIOXIDE

Oxycodone ER 10mg

BOXED WARNING

WARNING: ADDICTION, ABUSE AND MISUSE; LIFE-THREATENING RESPIRATORY DEPRESSION; ACCIDENTAL INGESTION; NEONATAL OPIOID WITHDRAWAL SYNDROME; CYTOCHROME P450 3A4 INTERACTION; AND RISKS FROM CONCOMITANT USE WITH BENZODIAZEPINES OR OTHER CNS DEPRESSANTS

Addiction, Abuse, and Misuse

OXYCODONE HCl EXTENDED-RELEASE TABLETS exposes patients and other users to the risks of opioid addiction, abuse, and misuse, which can lead to overdose and death. Assess each patient’s risk prior to prescribing OXYCODONE HCl EXTENDED-RELEASE TABLETS and monitor all patients regularly for the development of these behaviors and conditions [see Warnings and Precautions (5.1)].

Life-Threatening Respiratory Depression

Serious, life-threatening, or fatal respiratory depression may occur with use of OXYCODONE HCl EXTENDED-RELEASE TABLETS. Monitor for respiratory depression, especially during initiation of OXYCODONE HCl EXTENDED-RELEASE TABLETS or following a dose increase. Instruct patients to swallow OXYCODONE HCl EXTENDED-RELEASE TABLETS whole; crushing, chewing, or dissolving OXYCODONE HCl EXTENDED-RELEASE TABLETS can cause rapid release and absorption of a potentially fatal dose of oxycodone [see Warnings and Precautions (5.2)].

Accidental Ingestion

Accidental ingestion of even one dose of OXYCODONE HCl EXTENDED-RELEASE TABLETS, especially by children, can result in a fatal overdose of oxycodone [see Warnings and Precautions (5.2)].

Neonatal Opioid Withdrawal Syndrome

Prolonged use of OXYCODONE HCl EXTENDED-RELEASE TABLETS during pregnancy can result in neonatal opioid withdrawal syndrome, which may be life-threatening if not recognized and treated, and requires management according to protocols developed by neonatology experts. If opioid use is required for a prolonged period in a pregnant woman, advise the patient of the risk of neonatal opioid withdrawal syndrome and ensure that appropriate treatment will be available [see Warnings and Precautions (5.3)].

Cytochrome P450 3A4 Interaction

The concomitant use of OXYCODONE HCl EXTENDED-RELEASE TABLETS with all cytochrome P450 3A4 inhibitors may result in an increase in oxycodone plasma concentrations, which could increase or prolong adverse drug effects and may cause potentially fatal respiratory depression. In addition, discontinuation of a concomitantly used cytochrome P450 3A4 inducer may result in an increase in oxycodone plasma concentration. Monitor patients receiving OXYCODONE HCl EXTENDED-RELEASE TABLETS and any CYP3A4 inhibitor or inducer [see Warnings and Precautions (5.4), Drug Interactions (7), Clinical Pharmacology (12.3)].

Risks From Concomitant Use With Benzodiazepines Or Other CNS Depressants

Concomitant use of opioids with benzodiazepines or other central nervous system (CNS) depressants, including alcohol, may result in profound sedation, respiratory depression, coma, and death [see Warnings and Precautions (5.5), Drug Interactions (7)].

• Reserve concomitant prescribing of OXYCODONE HCl EXTENDED-RELEASE TABLETS and benzodiazepines or other CNS depressants for use in patients for whom alternative treatment options are inadequate.
• Limit dosages and durations to the minimum required.
• Follow patients for signs and symptoms of respiratory depression and sedation.

HIGHLIGHTS OF PRESCRIBING INFORMATION

These highlights do not include all the information needed to use OXYCODONE HCl EXTENDED-RELEASE TABLETS safely and effectively. See full prescribing information for OXYCODONE HCl EXTENDED-RELEASE TABLETS.
OXYCODONE HCl EXTENDED-RELEASE TABLETS, for oral use, CII
Initial U.S. Approval: 1950

WARNING: ADDICTION, ABUSE AND MISUSE; LIFE-THREATENING RESPIRATORY DEPRESSION; ACCIDENTAL INGESTION; NEONATAL OPIOID WITHDRAWAL SYNDROME; CYTOCHROME P450 3A4 INTERACTION; AND RISKS FROM CONCOMITANT USE WITH BENZODIAZEPINES OR OTHER CNS DEPRESSANTS

SEE FULL PRESCRIBING INFORMATION FOR COMPLETE BOXED WARNING.

•
OXYCODONE HCl EXTENDED-RELEASE TABLETS exposes users to risks of addiction, abuse and misuse, which can lead to overdose and death. Assess patient’s risk before prescribing and monitor regularly for these behaviors and conditions. (5.1)
•
Serious, life-threatening, or fatal respiratory depression may occur. Monitor closely, especially upon initiation or following a dose increase. Instruct patients to swallow OXYCODONE HCl EXTENDED-RELEASE TABLETS whole to avoid exposure to a potentially fatal dose of oxycodone. (5.2)
•
Accidental ingestion of OXYCODONE HCl EXTENDED-RELEASE TABLETS, especially by children, can result in a fatal overdose of oxycodone. (5.2)
•
Prolonged use of OXYCODONE HCl EXTENDED-RELEASE TABLETS during pregnancy can result in neonatal opioid withdrawal syndrome, which may be life-threatening if not recognized and treated. If prolonged opioid use is required in a pregnant woman, advise the patient of the risk of neonatal opioid withdrawal syndrome and ensure that appropriate treatment will be available. (5.3)
•
Concomitant use with CYP3A4 inhibitors (or discontinuation of CYP3A4 inducers) can result in a fatal overdose of oxycodone. (5.4, 7, 12.3)
•
Concomitant use of opioids with benzodiazepines or other central nervous system (CNS) depressants, including alcohol, may result in profound sedation, respiratory depression, coma, and death. Reserve concomitant prescribing for use in patients for whom alternative treatment options are inadequate; limit dosages and durations to the minimum required; and follow patients for signs and symptoms of respiratory depression and sedation. (5.5, 7)

RECENT MAJOR CHANGES

BOXED WARNING

12/2016

Indications and Usage (1)

12/2016

Dosage and Administration (2)

12/2016

Warnings and Precautions (5)

12/2016

INDICATIONS AND USAGE

OXYCODONE HCl EXTENDED-RELEASE TABLETS are an opioid agonist indicated for the management of pain severe enough to require daily, around-the-clock, long-term opioid treatment and for which alternative treatment options are inadequate in:

•
Adults; and
•
Opioid-tolerant pediatric patients 11 years of age and older who are already receiving and tolerate a minimum daily opioid dose of at least 20 mg oxycodone orally or its equivalent.

Limitations of Use

•
Because of the risks of addiction, abuse and misuse with opioids, even at recommended doses, and because of the greater risks of overdose and death with extended-release opioid formulations, reserve OXYCODONE HCl EXTENDED-RELEASE TABLETS for use in patients for whom alternative treatment options (e.g. non-opioid analgesics or immediate-release opioids) are ineffective, not tolerated, or would be otherwise inadequate to provide sufficient management of pain. (1)
•
OXYCODONE HCl EXTENDED-RELEASE TABLETS are not indicated as an as-needed (prn) analgesic. (1)

DOSAGE AND ADMINISTRATION

•
To be prescribed only by healthcare providers knowledgeable in use of potent opioids for management of chronic pain. (2.1)
•
OXYCODONE HCl EXTENDED-RELEASE TABLETS 80 mg tablets, a single dose greater than 40 mg, or a total daily dose greater than 80 mg are only for use in patients in whom tolerance to an opioid of comparable potency has been established. (2.1)
•
Patients considered opioid-tolerant are those taking, for one week or longer, at least 60 mg oral morphine per day, 25 mcg transdermal fentanyl per hour, 30 mg oral oxycodone per day, 8 mg oral hydromorphone per day, 25 mg oral oxymorphone per day, 60 mg oral hydrocodone per day, or an equianalgesic dose of another opioid. (2.1)
•
Use the lowest effective dosage for the shortest duration consistent with individual patient treatment goals (2.1).
•
Individualize dosing based on the severity of pain, patient response, prior analgesic experience, and risk factors for addiction, abuse, and misuse. (2.1)
•
Instruct patients to swallow tablets intact and not to cut, break, chew, crush, or dissolve tablets (risk of potentially fatal dose). (2.1, 5.1)
•
Instruct patients to take tablets one at a time, with enough water to ensure complete swallowing immediately after placing in mouth. (2.1, 5.10)
•
Do not abruptly discontinue OXYCODONE HCl EXTENDED-RELEASE TABLETS in a physically dependent patient. (2.9)
•
Adults: For opioid-naïve and opioid non-tolerant patients, initiate with 10 mg tablets orally every 12 hours. See full prescribing information for instructions on conversion from opioids to OXYCODONE HCl EXTENDED-RELEASE TABLETS, titration and maintenance of therapy. (2.2, 2.3, 2.5)
•
Pediatric Patients 11 Years of Age and Older
•
For use only in pediatric patients 11 years and older already receiving and tolerating opioids for at least 5 consecutive days with a minimum of 20 mg per day of oxycodone or its equivalent for at least two days immediately preceding dosing with OXYCODONE HCl EXTENDED-RELEASE TABLETS. (2.4)
•
See full prescribing information for instructions on conversion from opioids to OXYCODONE HCl EXTENDED-RELEASE TABLETS, titration and maintenance of therapy. (2.4, 2.5)
•
Geriatric Patients: In debilitated, opioid non-tolerant geriatric patients, initiate dosing at one third to one half the recommended starting dosage and titrate carefully. (2.7, 8.5)
•
Patients with Hepatic Impairment: Initiate dosing at one third to one half the recommended starting dosage and titrate carefully. (2.8, 8.6)

DOSAGE FORMS AND STRENGTHS

Extended-release tablets: 10 mg, 20 mg, 40 mg, and 80 mg (3)

CONTRAINDICATIONS

•
Significant respiratory depression (4)
•
Acute or severe bronchial asthma in an unmonitored setting or in absence of resuscitative equipment (4)
•
Known or suspected gastrointestinal obstruction, including paralytic ileus (4)
•
Hypersensitivity to oxycodone (4)

WARNINGS AND PRECAUTIONS

•
Life-Threatening Respiratory Depression in Patients with Chronic Pulmonary Disease or in Elderly, Cachectic, or Debilitated Patients: Monitor closely, particularly during initiation and titration. (5.6)
•
Adrenal Insufficiency: If diagnosed, treat with physiologic replacement of corticosteroids, and wean patient off of the opioid. (5.7)
•
Severe Hypotension: Monitor during dosage initiation and titration. Avoid use of OXYCODONE HCl EXTENDED-RELEASE TABLETS in patients with circulatory shock. (5.8)
•
Risks of Use in Patients with Increased Intracranial Pressure, Brain Tumors, Head Injury, or Impaired Consciousness: Monitor for sedation and respiratory depression. Avoid use of OXYCODONE HCl EXTENDED-RELEASE TABLETS in patients with impaired consciousness or coma. (5.9)
•
Risk of Obstruction in Patients who have Difficulty Swallowing or have Underlying GI Disorders that may Predispose them to Obstruction: Consider use of an alternative analgesic. (5.10)

ADVERSE REACTIONS

Most common adverse reactions (incidence >5%) were constipation, nausea, somnolence, dizziness, vomiting, pruritus, headache, dry mouth, asthenia, and sweating. (6.1)

To report SUSPECTED ADVERSE REACTIONS, contact TEVA USA, PHARMACOVIGILANCE at 1-866-832-8537 or drug.safety@tevapharm.com or FDA at 1-800-FDA-1088 or WWW.FDA.GOV/MEDWATCH.

DRUG INTERACTIONS

•
CNS Depressants: Concomitant use may cause hypotension, profound sedation, respiratory depression, coma, and death. If co-administration is required and the decision to begin OXYCODONE HCl EXTENDED-RELEASE TABLETS is made, start with 1/3 to 1/2 the recommended starting dosage, consider using a lower dosage of the concomitant CNS depressant, and monitor closely. (2.6, 5.5, 7)
•
Serotonergic Drugs: Concomitant use may result in serotonin syndrome. Discontinue OXYCODONE HCl EXTENDED-RELEASE TABLETS if serotonin syndrome is suspected. (7)
•
Mixed Agonist/Antagonist and Partial Agonist Opioid Analgesics: Avoid use with OXYCODONE HCl EXTENDED-RELEASE TABLETS because they may reduce analgesic effect of OXYCODONE HCl EXTENDED-RELEASE TABLETS or precipitate withdrawal symptoms. (5.13, 7)
•
Monoamine Oxidase Inhibitors (MAOIs): Can potentiate the effects of morphine. Avoid concomitant use in patients receiving MAOIs or within 14 days of stopping treatment with an MAOI. (7)

USE IN SPECIFIC POPULATIONS

Pregnancy: May cause fetal harm. (8.1)

Lactation: Not recommended. (8.2)

See 17 for PATIENT COUNSELING INFORMATION and Medication Guide.

Revised: 4/2017

FULL PRESCRIBING INFORMATION: CONTENTS*

WARNING: ADDICTION, ABUSE AND MISUSE; LIFE-THREATENING RESPIRATORY DEPRESSION; ACCIDENTAL INGESTION; NEONATAL OPIOID WITHDRAWAL SYNDROME; CYTOCHROME P450 3A4 INTERACTION; AND RISKS FROM CONCOMITANT USE WITH BENZODIAZEPINES OR OTHER CNS DEPRESSANTS
1 INDICATIONS AND USAGE
2 DOSAGE AND ADMINISTRATION
2.1 Important Dosage and Administration Instructions
2.2 Initial Dosage in Adults who are not Opioid Tolerant
2.3 Conversion from Opioids to OXYCODONE HCl EXTENDED-RELEASE TABLETS in Adults
2.4 Initial Dosage in Pediatric Patients 11 Years and Older
2.5 Titration and Maintenance of Therapy in Adults and Pediatric Patients 11 Years and Older
2.6 Dosage Modifications with Concomitant Use of Central Nervous System Depressants
2.7 Dosage Modifications in Geriatric Patients who are Debilitated and not Opioid-Tolerant
2.8 Dosage Modifications in Patients with Hepatic Impairment
2.9 Discontinuation of OXYCODONE HCl EXTENDED-RELEASE TABLETS
3 DOSAGE FORMS AND STRENGTHS
4 CONTRAINDICATIONS
5 WARNINGS AND PRECAUTIONS
5.1 Addiction, Abuse, and Misuse
5.2 Life-Threatening Respiratory Depression
5.3 Neonatal Opioid Withdrawal Syndrome
5.4 Risks of Concomitant Use or Discontinuation of Cytochrome P450 3A4 Inhibitors and Inducers
5.5 Risks from Concomitant Use with Benzodiazepines or Other CNS Depressants
5.6 Life-Threatening Respiratory Depression in Patients with Chronic Pulmonary Disease or in Elderly, Cachectic, or Debilitated Patients
5.7 Adrenal Insufficiency
5.8 Severe Hypotension
5.9 Risks of Use in Patients with Increased Intracranial Pressure, Brain Tumors, Head Injury, or Impaired Consciousness
5.10 Difficulty in Swallowing and Risk for Obstruction in Patients at Risk for a Small Gastrointestinal Lumen
5.11 Risks of Use in Patients with Gastrointestinal Conditions
5.12 Increased Risk of Seizures in Patients with Seizure Disorders
5.13 Withdrawal
5.14 Risks of Driving and Operating Machinery
5.15 Laboratory Monitoring
6 ADVERSE REACTIONS
6.1 Clinical Trial Experience
6.2 Postmarketing Experience
7 DRUG INTERACTIONS
8 USE IN SPECIFIC POPULATIONS
8.1 Pregnancy
8.2 Lactation
8.3 Females and Males of Reproductive Potential
8.4 Pediatric Use
8.5 Geriatric Use
8.6 Hepatic Impairment
8.7 Renal Impairment
8.8 Sex Differences
9 DRUG ABUSE AND DEPENDENCE
9.1 Controlled Substance
9.2 Abuse
9.3 Dependence
10 OVERDOSAGE
11 DESCRIPTION
12 CLINICAL PHARMACOLOGY
12.1 Mechanism of Action
12.2 Pharmacodynamics
12.3 Pharmacokinetics
13 NONCLINICAL TOXICOLOGY
13.1 Carcinogenesis, Mutagenesis, Impairment of Fertility
14 CLINICAL STUDIES
16 HOW SUPPLIED/STORAGE AND HANDLING
17 PATIENT COUNSELING INFORMATION
Oxycodone Hydrochloride Extended-release Tablets 10 mg, CII, 100s Label Text
Oxycodone Hydrochloride Extended-release Tablets 20 mg, CII, 100s Label Text
Oxycodone Hydrochloride Extended-release Tablets 40 mg, CII, 100s Label Text
Oxycodone Hydrochloride Extended-release Tablets 80 mg, CII, 100s Label Text

*
Sections or subsections omitted from the full prescribing information are not listed.

1 INDICATIONS AND USAGE

OXYCODONE HCl EXTENDED-RELEASE TABLETS are indicated for the management of pain severe enough to require daily, around-the-clock, long-term opioid treatment and for which alternative treatment options are inadequate in:

•
Adults; and
•
Opioid-tolerant pediatric patients 11 years of age and older who are already receiving and tolerate a minimum daily opioid dose of at least 20 mg oxycodone orally or its equivalent.

Limitations of Use

•
Because of the risks of addiction, abuse, and misuse with opioids, even at recommended doses, and because of the greater risks of overdose and death with extended-release opioid formulations [see Warnings and Precautions (5.1)], reserve OXYCODONE HCl EXTENDED-RELEASE TABLETS for use in patients for whom alternative treatment options (e.g., non-opioid analgesics or immediate-release opioids) are ineffective, not tolerated, or would be otherwise inadequate to provide sufficient management of pain.
•
OXYCODONE HCl EXTENDED-RELEASE TABLETS are not indicated as an as-needed (prn) analgesic.

2 DOSAGE AND ADMINISTRATION

2.1 Important Dosage and Administration Instructions

OXYCODONE HCl EXTENDED-RELEASE TABLETS should be prescribed only by healthcare professionals who are knowledgeable in the use of potent opioids for the management of chronic pain.

OXYCODONE HCl EXTENDED-RELEASE TABLETS 60 mg and 80 mg tablets, a single dose greater than 40 mg, or a total daily dose greater than 80 mg are only for use in patients in whom tolerance to an opioid of comparable potency has been established. Adult patients who are opioid tolerant are those receiving, for one week or longer, at least 60 mg oral morphine per day, 25 mcg transdermal fentanyl per hour, 30 mg oral oxycodone per day, 8 mg oral hydromorphone per day, 25 mg oral oxymorphone per day, 60 mg oral hydrocodone per day, or an equianalgesic dose of another opioid.

Use the lowest effective dosage for the shortest duration consistent with individual patient treatment goals [see Warnings and Precautions (5.1)].

Initiate the dosing regimen for each patient individually; taking into account the patient's severity of pain, patient response, prior analgesic treatment experience, and risk factors for addiction, abuse, and misuse [see Warnings and Precautions (5.1)].

Monitor patients closely for respiratory depression, especially within the first 24-72 hours of initiating therapy and following dosage increases with OXYCODONE HCl EXTENDED-RELEASE TABLETS and adjust the dosage accordingly [see Warnings and Precautions (5.2)].

Instruct patients to swallow OXYCODONE HCl EXTENDED-RELEASE TABLETS whole, one tablet at a time, with enough water to ensure complete swallowing immediately after placing in the mouth [see Patient Counseling Information (17)]. Instruct patients not to pre-soak, lick, or otherwise wet the tablet prior to placing in the mouth [see Warnings and Precautions (5.10)]. Cutting, breaking, crushing, chewing, or dissolving OXYCODONE HCl EXTENDED-RELEASE TABLETS will result in uncontrolled delivery of oxycodone and can lead to overdose or death [see Warnings and Precautions (5.1)].

OXYCODONE HCl EXTENDED-RELEASE TABLETS are administered orally every 12 hours.

2.2 Initial Dosage in Adults who are not Opioid Tolerant

The starting dosage for patients who are not opioid tolerant is OXYCODONE HCl EXTENDED-RELEASE TABLETS 10 mg orally every 12 hours.

Use of higher starting doses in patients who are not opioid tolerant may cause fatal respiratory depression [see Warnings and Precautions (5.2)].

2.3 Conversion from Opioids to OXYCODONE HCl EXTENDED-RELEASE TABLETS in Adults

Conversion from Other Oral Oxycodone Formulations to OXYCODONE HCl EXTENDED-RELEASE TABLETS

If switching from other oral oxycodone formulations to OXYCODONE HCl EXTENDED-RELEASE TABLETS, administer one half of the patient's total daily oral oxycodone dose as OXYCODONE HCl EXTENDED-RELEASE TABLETS every 12 hours.

Conversion from Other Opioids to OXYCODONE HCl EXTENDED-RELEASE TABLETS

Discontinue all other around-the-clock opioid drugs when OXYCODONE HCl EXTENDED-RELEASE TABLETS therapy is initiated.

There are no established conversion ratios for conversion from other opioids to OXYCODONE HCl EXTENDED-RELEASE TABLETS defined by clinical trials. Initiate dosing using OXYCODONE HCl EXTENDED-RELEASE TABLETS 10 mg orally every 12 hours.

It is safer to underestimate a patient’s 24-hour oral oxycodone requirements and provide rescue medication (e.g., immediate-release opioid) than to overestimate the 24-hour oral oxycodone dosage and manage an adverse reaction due to an overdose. While useful tables of opioid equivalents are readily available, there is substantial inter-patient variability in the relative potency of different opioids.

Close observation and frequent titration are warranted until pain management is stable on the new opioid. Monitor patients for signs and symptoms of opioid withdrawal and for signs of oversedation/toxicity after converting patients to OXYCODONE HCl EXTENDED-RELEASE TABLETS.

Conversion from Methadone to OXYCODONE HCl EXTENDED-RELEASE TABLETS

Close monitoring is of particular importance when converting from methadone to other opioid agonists. The ratio between methadone and other opioid agonists may vary widely as a function of previous dose exposure. Methadone has a long half-life and can accumulate in the plasma.

Conversion from Transdermal Fentanyl to OXYCODONE HCl EXTENDED-RELEASE TABLETS

Treatment with OXYCODONE HCl EXTENDED-RELEASE TABLETS can be initiated after the transdermal fentanyl patch has been removed for at least 18 hours. Although there has been no systematic assessment of such conversion, start with a conservative conversion: substitute 10 mg of OXYCODONE HCI EXTENDED-RELEASE TABLETS every 12 hours for each 25 mcg per hour fentanyl transdermal patch. Follow the patient closely during conversion from transdermal fentanyl to OXYCODONE HCl EXTENDED-RELEASE TABLETS, as there is limited documented experience with this conversion.

2.4 Initial Dosage in Pediatric Patients 11 Years and Older

The following dosing information is for use only in pediatric patients 11 years and older already receiving and tolerating opioids for at least five consecutive days. For the two days immediately preceding dosing with OXYCODONE HCl EXTENDED-RELEASE TABLETS, patients must be taking a minimum of 20 mg per day of oxycodone or its equivalent. OXYCODONE HCl EXTENDED-RELEASE TABLETS is not appropriate for use in pediatric patients requiring less than a 20 mg total daily dose. Table 1, based on clinical trial experience, displays the conversion factor when switching pediatric patients 11 years and older (under the conditions described above) from opioids to OXYCODONE HCl EXTENDED-RELEASE TABLETS.

Discontinue all other around-the-clock opioid drugs when OXYCODONE HCl EXTENDED-RELEASE TABLETS therapy is initiated.

There is substantial inter-patient variability in the relative potency of different opioid drugs and formulations. Therefore, a conservative approach is advised when determining the total daily dosage of OXYCODONE HCl EXTENDED-RELEASE TABLETS. It is safer to underestimate a patient’s 24-hour oral oxycodone requirements and provide rescue medication (e.g., immediate-release opioid) than to overestimate the 24-hour oral oxycodone requirements and manage an adverse reaction due to an overdose.

Consider the following when using the information in Table 1.

•
This is not a table of equianalgesic doses.
•
The conversion factors in this table are only for the conversion from one of the listed oral opioid analgesics to OXYCODONE HCl EXTENDED-RELEASE TABLETS.
•
The table cannot be used to convert from OXYCODONE HCl EXTENDED-RELEASE TABLETS to another opioid. Doing so will result in an over-estimation of the dose of the new opioid and may result in fatal overdose.
•
The formula for conversion from prior opioids, including oral oxycodone, to the daily dose of OXYCODONE HCl EXTENDED-RELEASE TABLETS is mg per day of prior opioid x factor = mg per day of OXYCODONE HCl EXTENDED-RELEASE TABLETS. Divide the calculated total daily dose by 2 to get the every-12-hour OXYCODONE HCl EXTENDED-RELEASE TABLETS dose. If rounding is necessary, always round the dose down to the nearest OXYCODONE HCl EXTENDED-RELEASE TABLET strength available.

Table 1: Conversion Factors When Switching Pediatric Patients 11 Years and Older to OXYCODONE HCl EXTENDED-RELEASE TABLETS

*
For patients receiving high-dose parenteral opioids, a more conservative conversion is warranted. For example, for high-dose parenteral morphine, use 1.5 instead of 3 as a multiplication factor.

Prior Opioid

Conversion Factor

Oral

Parenteral*

Oxycodone

1

--

Hydrocodone

0.9

--

Hydromorphone

4

20

Morphine

0.5

3

Tramadol

0.17

0.2

Step #1: To calculate the estimated total OXYCODONE HCl EXTENDED-RELEASE TABLETS daily dosage using Table 1:

•
For pediatric patients taking a single opioid, sum the current total daily dosage of the opioid and then multiply the total daily dosage by the approximate conversion factor to calculate the approximate OXYCODONE HCl EXTENDED-RELEASE TABLETS daily dosage.
•
For pediatric patients on a regimen of more than one opioid, calculate the approximate oxycodone dose for each opioid and sum the totals to obtain the approximate OXYCODONE HCl EXTENDED-RELEASE TABLETS daily dosage.
•
For pediatric patients on a regimen of fixed-ratio opioid/non-opioid analgesic products, use only the opioid component of these products in the conversion.

Step #2: If rounding is necessary, always round the dosage down to the nearest OXYCODONE HCl EXTENDED-RELEASE TABLET strength available and initiate OXYCODONE HCl EXTENDED-RELEASE TABLETS therapy with that dose. If the calculated OXYCODONE HCl EXTENDED-RELEASE TABLETS total daily dosage is less than 20 mg, there is no safe strength for conversion and do not initiate OXYCODONE HCl EXTENDED-RELEASE TABLETS.

Example conversion from a single opioid (e.g., hydrocodone) to OXYCODONE HCl EXTENDED-RELEASE TABLETS: Using the conversion factor of 0.9 for oral hydrocodone in Table 1, a total daily hydrocodone dosage of 50 mg is converted to 45 mg of oxycodone per day or 22.5 mg of OXYCODONE HCl EXTENDED-RELEASE TABLETS every 12 hours. After rounding down to the nearest strength available, the recommended OXYCODONE HCl EXTENDED-RELEASE TABLETS starting dosage is 20 mg every 12 hours.

Step #3: Close observation and titration are warranted until pain management is stable on the new opioid. Monitor patients for signs and symptoms of opioid withdrawal or for signs of over-sedation/toxicity after converting patients to OXYCODONE HCl EXTENDED-RELEASE TABLETS. [see Dosage and Administration (2.5)] for important instructions on titration and maintenance of therapy.

There is limited experience with conversion from transdermal fentanyl to OXYCODONE HCl EXTENDED-RELEASE TABLETS in pediatric patients 11 years and older. If switching from transdermal fentanyl patch to OXYCODONE HCl EXTENDED-RELEASE TABLETS, ensure that the patch has been removed for at least 18 hours prior to starting OXYCODONE HCl EXTENDED-RELEASE TABLETS. Although there has been no systematic assessment of such conversion, start with a conservative conversion: substitute 10 mg of OXYCODONE HCl EXTENDED-RELEASE TABLETS every 12 hours for each 25 mcg per hour fentanyl transdermal patch. Follow the patient closely during conversion from transdermal fentanyl to OXYCODONE HCl EXTENDED-RELEASE TABLETS.

If using asymmetric dosing, instruct patients to take the higher dose in the morning and the lower dose in the evening.

2.5 Titration and Maintenance of Therapy in Adults and Pediatric Patients 11 Years and Older

Individually titrate OXYCODONE HCl EXTENDED-RELEASE TABLETS to a dosage that provides adequate analgesia and minimizes adverse reactions. Continually reevaluate patients receiving OXYCODONE HCl EXTENDED-RELEASE TABLETS to assess the maintenance of pain control, signs and symptoms of opioid withdrawal, and adverse reactions, as well as monitoring for the development of addiction, abuse and misuse [see Warnings and Precautions (5.1)]. Frequent communication is important among the prescriber, other members of the healthcare team, the patient, and the caregiver/family during periods of changing analgesic requirements, including initial titration. During chronic therapy, periodically reassess the continued need for the use of opioid analgesics.

Patients who experience breakthrough pain may require a dosage adjustment of OXYCODONE HCl EXTENDED-RELEASE TABLETS or may need rescue medication with an appropriate dose of an immediate-release analgesic. If the level of pain increases after dose stabilization, attempt to identify the source of increased pain before increasing the OXYCODONE HCl EXTENDED-RELEASE TABLETS dosage. Because steady-state plasma concentrations are approximated in 1 day, OXYCODONE HCl EXTENDED-RELEASE TABLETS dosage may be adjusted every 1 to 2 days.

If unacceptable opioid-related adverse reactions are observed, consider reducing the dosage. Adjust the dosage to obtain an appropriate balance between management of pain and opioid-related adverse reactions.

There are no well-controlled clinical studies evaluating the safety and efficacy with dosing more frequently than every 12 hours. As a guideline for pediatric patients 11 years and older, the total daily oxycodone dosage usually can be increased by 25% of the current total daily dosage. As a guideline for adults, the total daily oxycodone dosage usually can be increased by 25% to 50% of the current total daily dosage, each time an increase is clinically indicated.

2.6 Dosage Modifications with Concomitant Use of Central Nervous System Depressants

If the patient is currently taking a central nervous system (CNS) depressant and the decision is made to begin OXYCODONE HCl EXTENDED-RELEASE TABLETS, start with one-third to one-half the recommended starting dosage of OXYCODONE HCl EXTENDED-RELEASE TABLETS, consider using a lower dosage of the concomitant CNS depressant, and monitor patients for signs of respiratory depression, sedation, and hypotension [see Warnings and Precautions (5.5), Drug Interactions (7)].

2.7 Dosage Modifications in Geriatric Patients who are Debilitated and not Opioid-Tolerant

For geriatric patients who are debilitated and not opioid tolerant, start dosing patients at one-third to one-half the recommended starting dosage and titrate the dosage cautiously [see Use in Specific Populations (8.5].

2.8 Dosage Modifications in Patients with Hepatic Impairment

For patients with hepatic impairment, start dosing patients at one-third to one-half the recommended starting dosage and titrate the dosage carefully. Monitor for signs of respiratory depression, sedation, and hypotension [see Use in Specific Populations, (8.6), Clinical Pharmacology (12.3)].

2.9 Discontinuation of OXYCODONE HCl EXTENDED-RELEASE TABLETS

When the patient no longer requires therapy with OXYCODONE HCl EXTENDED-RELEASE TABLETS, taper the dosage gradually, by 25% to 50% every 2 to 4 days, while monitoring for signs and symptoms of withdrawal. If a patient develops these signs or symptoms, raise the dose to the previous level and taper more slowly, either by increasing the interval between decreases, decreasing the amount of change in dose, or both. Do not abruptly discontinue OXYCODONE HCl EXTENDED-RELEASE TABLETS [see Warnings and Precautions (5.13), Drug Abuse and Dependence (9.3)].

3 DOSAGE FORMS AND STRENGTHS

Extended-release tablets: 10 mg, 20 mg, 40 mg, and 80 mg

•
10 mg film-coated extended-release tablets (round, white-colored, bi-convex tablets debossed with OP on one side and 10 on the other)
•
20 mg film-coated extended-release tablets (round, pink-colored, bi-convex tablets debossed with OP on one side and 20 on the other)
•
40 mg film-coated extended-release tablets (round, yellow-colored, bi-convex tablets debossed with OP on one side and 40 on the other)
•
80 mg film-coated extended-release tablets (round, green-colored, bi-convex tablets debossed with OP on one side and 80 on the other)

4 CONTRAINDICATIONS

OXYCODONE HCl EXTENDED-RELEASE TABLETS are contraindicated in patients with:

•
Significant respiratory depression [see Warnings and Precautions (5.2)]
•
Acute or severe bronchial asthma in an unmonitored setting or in the absence of resuscitative equipment [see Warnings and Precautions (5.6)]
•
Known or suspected gastrointestinal obstruction, including paralytic ileus [see Warnings and Precautions (5.11)]
•
Hypersensitivity (e.g., anaphylaxis) to oxycodone [see Adverse Reactions (6.2)]

5 WARNINGS AND PRECAUTIONS

5.1 Addiction, Abuse, and Misuse

OXYCODONE HCl EXTENDED-RELEASE TABLETS contains oxycodone, a Schedule II controlled substance. As an opioid, OXYCODONE HCl EXTENDED-RELEASE TABLETS expose users to the risks of addiction, abuse, and misuse. Because extended-release products such as OXYCODONE HCl EXTENDED-RELEASE TABLETS deliver the opioid over an extended period of time, there is a greater risk for overdose and death due to the larger amount of oxycodone present [see Drug Abuse and Dependence (9)].

Although the risk of addiction in any individual is unknown, it can occur in patients appropriately prescribed OXYCODONE HCl EXTENDED-RELEASE TABLETS. Addiction can occur at recommended doses and if the drug is misused or abused.

Assess each patient’s risk for opioid addiction, abuse, or misuse prior to prescribing OXYCODONE HCl EXTENDED-RELEASE TABLETS, and monitor all patients receiving OXYCODONE HCl EXTENDED-RELEASE TABLETS for the development of these behaviors and conditions. Risks are increased in patients with a personal or family history of substance abuse (including drug or alcohol abuse or addiction) or mental illness (e.g., major depression). The potential for these risks should not, however, prevent the proper management of pain in any given patient. Patients at increased risk may be prescribed opioids such as OXYCODONE HCl EXTENDED-RELEASE TABLETS, but use in such patients necessitates intensive counseling about the risks and proper use of OXYCODONE HCl EXTENDED-RELEASE TABLETS along with intensive monitoring for signs of addiction, abuse, and misuse.

Abuse or misuse of OXYCODONE HCl EXTENDED-RELEASE TABLETS by crushing, chewing, snorting, or injecting the dissolved product will result in the uncontrolled delivery of oxycodone and can result in overdose and death [see Overdosage (10)].

Opioids are sought by drug abusers and people with addiction disorders and are subject to criminal diversion. Consider these risks when prescribing or dispensing OXYCODONE HCl EXTENDED-RELEASE TABLETS. Strategies to reduce these risks include prescribing the drug in the smallest appropriate quantity and advising the patient on the proper disposal of unused drug [see Patient Counseling Information (17)]. Contact local state professional licensing board or state controlled substances authority for information on how to prevent and detect abuse or diversion of this product.

5.2 Life-Threatening Respiratory Depression

Serious, life-threatening, or fatal respiratory depression has been reported with the use of opioids, even when used as recommended. Respiratory depression, if not immediately recognized and treated, may lead to respiratory arrest and death. Management of respiratory depression may include close observation, supportive measures, and use of opioid antagonists, depending on the patient’s clinical status [see Overdosage (10)]. Carbon dioxide (CO2) retention from opioid-induced respiratory depression can exacerbate the sedating effects of opioids.

While serious, life-threatening, or fatal respiratory depression can occur at any time during the use of OXYCODONE HCl EXTENDED-RELEASE TABLETS, the risk is greatest during the initiation of therapy or following a dosage increase. Monitor patients closely for respiratory depression, especially within the first 24-72 hours of initiating therapy with and following dosage increases of OXYCODONE HCl EXTENDED-RELEASE TABLETS.

To reduce the risk of respiratory depression, proper dosing and titration of OXYCODONE HCl EXTENDED-RELEASE TABLETS are essential [see Dosage and Administration (2)]. Overestimating the OXYCODONE HCl EXTENDED-RELEASE TABLETS dosage when converting patients from another opioid product can result in a fatal overdose with the first dose.

Accidental ingestion of even one dose of OXYCODONE HCl EXTENDED-RELEASE TABLETS, especially by children, can result in respiratory depression and death due to an overdose of oxycodone.

5.3 Neonatal Opioid Withdrawal Syndrome

Prolonged use of OXYCODONE HCl EXTENDED-RELEASE TABLETS during pregnancy can result in withdrawal in the neonate. Neonatal opioid withdrawal syndrome, unlike opioid withdrawal syndrome in adults, may be life-threatening if not recognized and treated, and requires management according to protocols developed by neonatology experts. Observe newborns for signs of neonatal opioid withdrawal syndrome and manage accordingly. Advise pregnant women using opioids for a prolonged period of the risk of neonatal opioid withdrawal syndrome and ensure that appropriate treatment will be available [see Use in Specific Populations (8.1), Patient Counseling Information (17)].

5.4 Risks of Concomitant Use or Discontinuation of Cytochrome P450 3A4 Inhibitors and Inducers

Concomitant use of OXYCODONE HCl EXTENDED-RELEASE TABLETS with a CYP3A4 inhibitor, such as macrolide antibiotics (e.g., erythromycin), azole-antifungal agents (e.g., ketoconazole), and protease inhibitors (e.g., ritonavir), may increase plasma concentrations of oxycodone and prolong opioid adverse reactions, which may cause potentially fatal respiratory depression [see Warnings and Precautions (5.2)], particularly when an inhibitor is added after a stable dose of OXYCODONE HCl EXTENDED-RELEASE TABLETS is achieved. Similarly, discontinuation of a CYP3A4 inducer, such as rifampin, carbamazepine, and phenytoin, in OXYCODONE HCl EXTENDED-RELEASE TABLETS -treated patients may increase oxycodone plasma concentrations and prolong opioid adverse reactions. When using OXYCODONE HCl EXTENDED-RELEASE TABLETS with CYP3A4 inhibitors or discontinuing CYP3A4 inducers in OXYCODONE HCl EXTENDED-RELEASE TABLETS -treated patients, monitor patients closely at frequent intervals and consider dosage reduction of OXYCODONE HCl EXTENDED-RELEASE TABLETS until stable drug effects are achieved [see Drug Interactions (7)].

Concomitant use of OXYCODONE HCl EXTENDED-RELEASE TABLETS with CYP3A4 inducers or discontinuation of a CYP3A4 inhibitor could decrease oxycodone plasma concentrations, decrease opioid efficacy or, possibly, lead to a withdrawal syndrome in a patient who had developed physical dependence to oxycodone. When using OXYCODONE HCl EXTENDED-RELEASE TABLETS with CYP3A4 inducers or discontinuing CYP3A4 inhibitors, monitor patients closely at frequent intervals and consider increasing the opioid dosage if needed to maintain adequate analgesia or if symptoms of opioid withdrawal occur [see Drug Interactions (7)].

5.5 Risks from Concomitant Use with Benzodiazepines or Other CNS Depressants

Profound sedation, respiratory depression, coma, and death may result if OXYCODONE HCl EXTENDED-RELEASE TABLETS are used concomitantly with alcohol or other central nervous system (CNS) depressants (e.g., non-benzodiazepines sedatives/hypnotics, anxiolytics, tranquilizers, muscle relaxants, general anesthetics, antipsychotics, other opioids, alcohol). Because of these risks, reserve concomitant prescribing of these drugs for use in patients for whom alternative treatment options are inadequate.

Observational studies have demonstrated that concomitant use of opioid analgesics and benzodiazepines increases the risk of drug-related mortality compared to use of opioid analgesics alone. Because of similar pharmacological properties, it is reasonable to expect similar risk with the concomitant use of other CNS depressant drugs with opioid analgesics [see Drug Interactions (7)].

If the decision is made to prescribe a benzodiazepine or other CNS depressant concomitantly with an opioid analgesic, prescribe the lowest effective dosages and minimum durations of concomitant use. In patients already receiving an opioid analgesic, prescribe a lower initial dose of the benzodiazepine or other CNS depressant than indicated in the absence of an opioid, and titrate based on clinical response. If an opioid analgesic is initiated in a patient already taking a benzodiazepine or other CNS depressant, prescribe a lower initial dose of the opioid analgesic, and titrate based on clinical response. Follow patients closely for signs and symptoms of respiratory depression and sedation.

Advise both patients and caregivers about the risks of respiratory depression and sedation when OXYCODONE HCl EXTENDED-RELEASE TABLETS is used with benzodiazepines or other CNS depressants (including alcohol and illicit drugs). Advise patients not to drive or operate heavy machinery until the effects of concomitant use of the benzodiazepine or other CNS depressant have been determined. Screen patients for risk of substance use disorders, including opioid abuse and misuse, and warn them of the risk for overdose and death associated with the use of additional CNS depressants including alcohol and illicit drugs [see Drug Interactions (7), Patient Counseling Information (17)].

5.6 Life-Threatening Respiratory Depression in Patients with Chronic Pulmonary Disease or in Elderly, Cachectic, or Debilitated Patients

The use of OXYCODONE HCl EXTENDED-RELEASE TABLETS in patients with acute or severe bronchial asthma in an unmonitored setting or in the absence of resuscitative equipment is contraindicated.

Patients with Chronic Pulmonary Disease: OXYCODONE HCl EXTENDED-RELEASE TABLETS -treated patients with significant chronic obstructive pulmonary disease or cor pulmonale, and those with a substantially decreased respiratory reserve, hypoxia, hypercapnia, or pre-existing respiratory depression are at increased risk of decreased respiratory drive including apnea, even at recommended dosages of OXYCODONE HCl EXTENDED-RELEASE TABLETS [see Warnings and Precautions (5.2)].

Elderly, Cachectic, or Debilitated Patients: Life-threatening respiratory depression is more likely to occur in elderly, cachectic, or debilitated patients because they may have altered pharmacokinetics or altered clearance compared to younger, healthier patients [see Warnings and Precautions (5.2)].

Monitor such patients closely, particularly when initiating and titrating OXYCODONE HCl EXTENDED-RELEASE TABLETS and when OXYCODONE HCl EXTENDED-RELEASE TABLETS are given concomitantly with other drugs that depress respiration [see Warnings and Precautions (5.2, 5.5)]. Alternatively, consider the use of non-opioid analgesics in these patients.

5.7 Adrenal Insufficiency

Cases of adrenal insufficiency have been reported with opioid use, more often following greater than one month of use. Presentation of adrenal insufficiency may include non-specific symptoms and signs including nausea, vomiting, anorexia, fatigue, weakness, dizziness, and low blood pressure. If adrenal insufficiency is suspected, confirm the diagnosis with diagnostic testing as soon as possible. If adrenal insufficiency is diagnosed, treat with physiologic replacement doses of corticosteroids. Wean the patient off of the opioid to allow adrenal function to recover and continue corticosteroid treatment until adrenal function recovers. Other opioids may be tried as some cases reported use of a different opioid without recurrence of adrenal insufficiency. The information available does not identify any particular opioids as being more likely to be associated with adrenal insufficiency.

5.8 Severe Hypotension

OXYCODONE HCl EXTENDED-RELEASE TABLETS may cause severe hypotension, including orthostatic hypotension and syncope in ambulatory patients. There is an increased risk in patients whose ability to maintain blood pressure has already been compromised by a reduced blood volume or concurrent administration of certain CNS depressant drugs (e.g., phenothiazines or general anesthetics) [see Drug Interactions (7)]. Monitor these patients for signs of hypotension after initiating or titrating the dosage of OXYCODONE HCl EXTENDED-RELEASE TABLETS. In patients with circulatory shock, OXYCODONE HCl EXTENDED-RELEASE TABLETS may cause vasodilation that can further reduce cardiac output and blood pressure. Avoid the use of OXYCODONE HCl EXTENDED-RELEASE TABLETS in patients with circulatory shock.

5.9 Risks of Use in Patients with Increased Intracranial Pressure, Brain Tumors, Head Injury, or Impaired Consciousness

In patients who may be susceptible to the intracranial effects of CO2 retention (e.g., those with evidence of increased intracranial pressure or brain tumors), OXYCODONE HCl EXTENDED-RELEASE TABLETS may reduce respiratory drive, and the resultant CO2 retention can further increase intracranial pressure. Monitor such patients for signs of sedation and respiratory depression, particularly when initiating therapy with OXYCODONE HCl EXTENDED-RELEASE TABLETS.

Opioids may also obscure the clinical course in a patient with a head injury. Avoid the use of OXYCODONE HCl EXTENDED-RELEASE TABLETS in patients with impaired consciousness or coma.

5.10 Difficulty in Swallowing and Risk for Obstruction in Patients at Risk for a Small Gastrointestinal Lumen

There have been post-marketing reports of difficulty in swallowing OXYCODONE HCl EXTENDED-RELEASE TABLETS. These reports included choking, gagging, regurgitation and tablets stuck in the throat. Instruct patients not to pre-soak, lick, or otherwise wet OXYCODONE HCl EXTENDED-RELEASE TABLETS prior to placing in the mouth, and to take one tablet at a time with enough water to ensure complete swallowing immediately after placing in the mouth.

There have been rare post-marketing reports of cases of intestinal obstruction, and exacerbation of diverticulitis, some of which have required medical intervention to remove the tablet. Patients with underlying GI disorders such as esophageal cancer or colon cancer with a small gastrointestinal lumen are at greater risk of developing these complications. Consider use of an alternative analgesic in patients who have difficulty swallowing and patients at risk for underlying GI disorders resulting in a small gastrointestinal lumen.

5.11 Risks of Use in Patients with Gastrointestinal Conditions

OXYCODONE HCl EXTENDED-RELEASE TABLETS are contraindicated in patients with known or suspected gastrointestinal obstruction, including paralytic ileus.

The oxycodone in OXYCODONE HCl EXTENDED-RELEASE TABLETS may cause spasm of the sphincter of Oddi. Opioids may cause increases in the serum amylase. Monitor patients with biliary tract disease, including acute pancreatitis, for worsening symptoms.

5.12 Increased Risk of Seizures in Patients with Seizure Disorders

The oxycodone in OXYCODONE HCl EXTENDED-RELEASE TABLETS may increase the frequency of seizures in patients with seizure disorders, and may increase the risk of seizures occurring in other clinical settings associated with seizures. Monitor patients with a history of seizure disorders for worsened seizure control during OXYCODONE HCl EXTENDED-RELEASE TABLETS therapy.

5.13 Withdrawal

Avoid the use of mixed agonist/antagonist (e.g.., pentazocine, nalbuphine, and butorphanol) or partial agonist (e.g., buprenorphine) analgesics in patients who are receiving a full opioid agonist analgesic, including OXYCODONE HCl EXTENDED-RELEASE TABLETS. In these patients, mixed agonist/antagonist and partial agonist analgesics may reduce the analgesic effect and/or may precipitate withdrawal symptoms.

When discontinuing OXYCODONE HCl EXTENDED-RELEASE TABLETS, gradually taper the dosage [see Dosage and Administration (2.9)]. Do not abruptly discontinue OXYCODONE HCl EXTENDED-RELEASE TABLETS [see Drug Abuse and Dependence (9.3)].

5.14 Risks of Driving and Operating Machinery

OXYCODONE HCl EXTENDED-RELEASE TABLETS may impair the mental or physical abilities needed to perform potentially hazardous activities such as driving a car or operating machinery. Warn patients not to drive or operate dangerous machinery unless they are tolerant to the effects of OXYCODONE HCl EXTENDED-RELEASE TABLETS and know how they will react to the medication [see Patient Counseling Information (17)].

5.15 Laboratory Monitoring

Not every urine drug test for “opioids” or “opiates” detects oxycodone reliably, especially those designed for in-office use. Further, many laboratories will report urine drug concentrations below a specified “cut-off” value as “negative”. Therefore, if urine testing for oxycodone is considered in the clinical management of an individual patient, ensure that the sensitivity and specificity of the assay is appropriate, and consider the limitations of the testing used when interpreting results.

6 ADVERSE REACTIONS

The following serious adverse reactions are described elsewhere in the labeling:

▪
Addiction, Abuse, and Misuse [see Warnings and Precautions (5.1)]
▪
Life-Threatening Respiratory Depression [see Warnings and Precautions (5.2)]
▪
Neonatal Opioid Withdrawal Syndrome [see Warnings and Precautions (5.3)]
▪
Interactions With Benzodiazepines and Other CNS Depressants [see Warnings and Precautions (5.5)]
▪
Adrenal Insufficiency [see Warnings and Precautions (5.7)]
▪
Severe Hypotension [see Warnings and Precautions (5.8)]
▪
Gastrointestinal Adverse Reactions [see Warnings and Precautions (5.10, 5.11)]
▪
Seizures [see Warnings and Precautions (5.12)]
▪
Withdrawal [see Warnings and Precautions (5.13)]

6.1 Clinical Trial Experience

Adult Clinical Trial Experience

Because clinical trials are conducted under widely varying conditions, adverse reaction rates observed in the clinical trials of a drug cannot be directly compared to rates in the clinical trials of another drug and may not reflect the rates observed in practice.

The safety of OXYCODONE HCl EXTENDED-RELEASE TABLETS was evaluated in double-blind clinical trials involving 713 patients with moderate to severe pain of various etiologies. In open-label studies of cancer pain, 187 patients received OXYCODONE HCl EXTENDED-RELEASE TABLETS in total daily doses ranging from 20 mg to 640 mg per day. The average total daily dose was approximately 105 mg per day.

OXYCODONE HCl EXTENDED-RELEASE TABLETS may increase the risk of serious adverse reactions such as those observed with other opioid analgesics, including respiratory depression, apnea, respiratory arrest, circulatory depression, hypotension, or shock [see Overdosage (10)].

The most common adverse reactions (>5%) reported by patients in clinical trials comparing OXYCODONE HCl EXTENDED-RELEASE TABLETS with placebo are shown in Table 2 below:

Table 2: Common Adverse Reactions (>5%)

Adverse Reaction

OXYCODONE HCl EXTENDED-RELEASE TABLETS
(n=227)

Placebo
(n=45)

(%)

(%)

Constipation

(23)

(7)

Nausea

(23)

(11)

Somnolence

(23)

(4)

Dizziness

(13)

(9)

Pruritus

(13)

(2)

Vomiting

(12)

(7)

Headache

(7)

(7)

Dry Mouth

(6)

(2)

Asthenia

(6)

-

Sweating

(5)

(2)

In clinical trials, the following adverse reactions were reported in patients treated with OXYCODONE HCl EXTENDED-RELEASE TABLETS with an incidence between 1% and 5%:

Gastrointestinal disorders: abdominal pain, diarrhea, dyspepsia, gastritis

General disorders and administration site conditions: chills, fever

Metabolism and nutrition disorders: anorexia

Musculoskeletal and connective tissue disorders: twitching

Psychiatric disorders: abnormal dreams, anxiety, confusion, dysphoria, euphoria, insomnia, nervousness, thought abnormalities

Respiratory, thoracic and mediastinal disorders: dyspnea, hiccups

Skin and subcutaneous tissue disorders: rash

Vascular disorders: postural hypotension

The following adverse reactions occurred in less than 1% of patients involved in clinical trials:

Blood and lymphatic system disorders: lymphadenopathy

Ear and labyrinth disorders: tinnitus

Eye disorders: abnormal vision

Gastrointestinal disorders: dysphagia, eructation, flatulence, gastrointestinal disorder, increased appetite, stomatitis

General disorders and administration site conditions: withdrawal syndrome (with and without seizures), edema, peripheral edema, thirst, malaise, chest pain, facial edema

Injury, poisoning and procedural complications: accidental injury

Investigations: ST depression

Metabolism and nutrition disorders: dehydration

Nervous system disorders: syncope, migraine, abnormal gait, amnesia, hyperkinesia, hypoesthesia, hypotonia, paresthesia, speech disorder, stupor, tremor, vertigo, taste perversion

Psychiatric disorders: depression, agitation, depersonalization, emotional lability, hallucination

Renal and urinary disorders: dysuria, hematuria, polyuria, urinary retention

Reproductive system and breast disorders: impotence

Respiratory, thoracic and mediastinal disorders: cough increased, voice alteration

Skin and subcutaneous tissue disorders: dry skin, exfoliative dermatitis

Clinical Trial Experience in Pediatric Patients 11 Years and Older

The safety of OXYCODONE HCl EXTENDED-RELEASE TABLETS has been evaluated in one clinical trial with 140 patients 11 to 16 years of age. The median duration of treatment was approximately three weeks. The most frequently reported adverse events were vomiting, nausea, headache, pyrexia, and constipation.

Table 3 includes a summary of the incidence of treatment emergent adverse events reported in ≥5% of patients.

Table 3: Incidence of Adverse Reactions Reported in ≥ 5.0% Patients 11 to 16 Years

System Organ Class
Preferred Term

11 to 16 Years
(N=140)
n (%)

Any Adverse Event >= 5%

71 (51)

GASTROINTESTINAL DISORDERS

56 (40)

Vomiting

30 (21)

Nausea

21 (15)

Constipation

13 (9)

Diarrhea

8 (6)

GENERAL DISORDERS AND ADMINISTRATION SITE CONDITIONS

32 (23)

Pyrexia

15 (11)

METABOLISM AND NUTRITION DISORDERS

9 (6)

Decreased appetite

7 (5)

NERVOUS SYSTEM DISORDERS

37 (26)

Headache

20 (14)

Dizziness

12 (9)

SKIN AND SUBCUTANEOUS TISSUE DISORDERS

23 (16)

Pruritus

8 (6)

The following adverse reactions occurred in a clinical trial of OXYCODONE HCl EXTENDED-RELEASE TABLETS in patients 11 to 16 years of age with an incidence between ≥1.0% and < 5.0%. Events are listed within each System/Organ Class.

Blood and lymphatic system disorders: febrile neutropenia, neutropenia

Cardiac disorders:tachycardia

Gastrointestinal disorders:abdominal pain, gastroesophageal reflux disease

General disorders and administration site conditions:fatigue, pain, chills, asthenia

Injury, poisoning, and procedural complications:procedural pain, seroma

Investigations:oxygen saturation decreased, alanine aminotransferase increased, hemoglobin decreased, platelet count decreased, neutrophil count decreased, red blood cell count decreased, weight decreased

Metabolic and nutrition disorders:hypochloremia, hyponatremia

Musculoskeletal and connective tissue disorders:pain in extremity, musculoskeletal pain

Nervous system disorders:somnolence, hypoesthesia, lethargy, paresthesia

Psychiatric disorders:insomnia, anxiety, depression, agitation

Renal and urinary disorders:dysuria, urinary retention

Respiratory, thoracic, and mediastinal disorders:oropharyngeal pain

Skin and subcutaneous tissue disorders:hyperhidrosis, rash

6.2 Postmarketing Experience

The following adverse reactions have been identified during post-approval use of extended-release oxycodone. Because these reactions are reported voluntarily from a population of uncertain size, it is not always possible to reliably estimate their frequency or establish a causal relationship to drug exposure.

Abuse, addiction, aggression, amenorrhea, cholestasis, completed suicide, death, dental caries, increased hepatic enzymes, hyperalgesia, hypogonadism, hyponatremia, ileus, intentional overdose, mood altered, muscular hypertonia, overdose, palpitations (in the context of withdrawal), seizures, suicidal attempt, suicidal ideation, syndrome of inappropriate antidiuretic hormone secretion, and urticaria.

In addition to the events listed above, the following have also been reported, potentially due to the swelling and hydrogelling property of the tablet: choking, gagging, regurgitation, tablets stuck in the throat and difficulty swallowing the tablet.

Serotonin syndrome: Cases of serotonin syndrome, a potentially life-threatening condition, have been reported during concomitant use of opioids with serotonergic drugs.

Adrenal insufficiency: Cases of adrenal insufficiency have been reported with opioid use, more often following greater than one month of use.

Anaphylaxis: Anaphylaxis has been reported with ingredients contained in OXYCODONE HCl EXTENDED-RELEASE TABLETS.

Androgen deficiency: Cases of androgen deficiency have occurred with chronic use of opioids [see Clinical Pharmacology (12.2)].

7 DRUG INTERACTIONS

Table 4 includes clinically significant drug interactions with OXYCODONE HCl EXTENDED-RELEASE TABLETS.

Table 4: Clinically Significant Drug Interactions with OXYCODONE HCl EXTENDED-RELEASE TABLETS

Inhibitors of CYP3A4 and CYP2D6

Clinical Impact:

The concomitant use of OXYCODONE HCl EXTENDED-RELEASE TABLETS and CYP3A4 inhibitors can increase the plasma concentration of oxycodone, resulting in increased or prolonged opioid effects. These effects could be more pronounced with concomitant use of OXYCODONE HCl EXTENDED-RELEASE TABLETS and CYP2D6 and CYP3A4 inhibitors, particularly when an inhibitor is added after a stable dose of OXYCODONE HCl EXTENDED-RELEASE TABLETS is achieved [see Warnings and Precautions (5.4)].

After stopping a CYP3A4 inhibitor, as the effects of the inhibitor decline, the oxycodone plasma concentration will decrease [see Clinical Pharmacology (12.3)], resulting in decreased opioid efficacy or a withdrawal syndrome in patients who had developed physical dependence to oxycodone.

Intervention:

If concomitant use is necessary, consider dosage reduction of OXYCODONE HCl EXTENDED-RELEASE TABLETS until stable drug effects are achieved. Monitor patients for respiratory depression and sedation at frequent intervals.

If a CYP3A4 inhibitor is discontinued, consider increasing the OXYCODONE HCl EXTENDED-RELEASE TABLETS dosage until stable drug effects are achieved. Monitor for signs of opioid withdrawal.

Examples

Macrolide antibiotics (e.g., erythromycin), azole-antifungal agents (e.g. ketoconazole), protease inhibitors (e.g., ritonavir)

CYP3A4 Inducers

Clinical Impact:

The concomitant use of OXYCODONE HCl EXTENDED-RELEASE TABLETS and CYP3A4 inducers can decrease the plasma concentration of oxycodone [see Clinical Pharmacology (12.3)], resulting in decreased efficacy or onset of a withdrawal syndrome in patients who have developed physical dependence to oxycodone [see Warnings and Precautions (5.4)].

After stopping a CYP3A4 inducer, as the effects of the inducer decline, the oxycodone plasma concentration will increase [see Clinical Pharmacology (12.3)], which could increase or prolong both the therapeutic effects and adverse reactions, and may cause serious respiratory depression.

Intervention:

If concomitant use is necessary, consider increasing the OXYCODONE HCl EXTENDED-RELEASE TABLETS dosage until stable drug effects are achieved. Monitor for signs of opioid withdrawal. If a CYP3A4 inducer is discontinued, consider OXYCODONE HCl EXTENDED-RELEASE TABLETS dosage reduction and monitor for signs of respiratory depression.

Examples:

Rifampin, carbamazepine, phenytoin

Benzodiazepines and Other Central Nervous System (CNS) Depressants

Clinical Impact:

Due to additive pharmacologic effect, the concomitant use of benzodiazepines or other CNS depressants, including alcohol, can increase the risk of hypotension, respiratory depression, profound sedation, coma, and death.

Intervention:

Reserve concomitant prescribing of these drugs for use in patients for whom alternative treatment options are inadequate. Limit dosages and durations to the minimum required. Follow patients closely for signs of respiratory depression and sedation [see Dosage and Administration (2.6), Warnings and Precautions(5.5)].

Examples:

Benzodiazepines and other sedatives/hypnotics, anxiolytics, tranquilizers, muscle relaxants, general anesthetics, antipsychotics, other opioids, alcohol.

Serotonergic Drugs

Clinical Impact:

The concomitant use of opioids with other drugs that affect the serotonergic neurotransmitter system has resulted in serotonin syndrome.

Intervention:

If concomitant use is warranted, carefully observe the patient, particularly during treatment initiation and dose adjustment. Discontinue OXYCODONE HCl EXTENDED-RELEASE TABLETS if serotonin syndrome is suspected.

Examples:

Selective serotonin reuptake inhibitors (SSRIs), serotonin and norepinephrine reuptake inhibitors (SNRIs), tricyclic antidepressants (TCAs), triptans, 5-HT3 receptor antagonists, drugs that affect the serotonin neurotransmitter system (e.g., mirtazapine, trazodone, tramadol), monoamine oxidase (MAO) inhibitors (those intended to treat psychiatric disorders and also others, such as linezolid and intravenous methylene blue).

Monoamine Oxidase Inhibitors (MAOIs)

Clinical Impact:

MAOI interactions with opioids may manifest as serotonin syndrome or opioid toxicity (e.g., respiratory depression, coma) [see Warnings and Precautions (5.2)].

Intervention:

The use of OXYCODONE HCl EXTENDED-RELEASE TABLETS is not recommended for patients taking MAOIs or within 14 days of stopping such treatment.

Examples:

phenelzine, tranylcypromine, linezolid

Mixed Agonist/Antagonist and Partial Agonist Opioid Analgesics

Clinical Impact:

May reduce the analgesic effect of OXYCODONE HCl EXTENDED-RELEASE TABLETS and/or precipitate withdrawal symptoms.

Intervention:

Avoid concomitant use.

Examples:

butorphanol, nalbuphine, pentazocine, buprenorphine

Muscle Relaxants

Clinical Impact:

Oxycodone may enhance the neuromuscular blocking action of skeletal muscle relaxants and produce an increased degree of respiratory depression.

Intervention:

Monitor patients for signs of respiratory depression that may be greater than otherwise expected and decrease the dosage of OXYCODONE HCl EXTENDED-RELEASE TABLETS and/or the muscle relaxant as necessary.

Diuretics

Clinical Impact:

Opioids can reduce the efficacy of diuretics by inducing the release of antidiuretic hormone.

Intervention:

Monitor patients for signs of diminished diuresis and/or effects on blood pressure and increase the dosage of the diuretic as needed.

Anticholinergic Drugs

Clinical Impact:

The concomitant use of anticholinergic drugs may increase risk of urinary retention and/or severe constipation, which may lead to paralytic ileus.

Intervention:

Monitor patients for signs of urinary retention or reduced gastric motility when OXYCODONE HCl EXTENDED-RELEASE TABLETS is used concomitantly with anticholinergic drugs.

8 USE IN SPECIFIC POPULATIONS

8.1 Pregnancy

Risk Summary

Prolonged use of opioid analgesics during pregnancy may cause neonatal opioid withdrawal syndrome [see Warnings and Precautions (5.3)]. There are no available data with OXYCODONE HCl EXTENDED-RELEASE TABLETS in pregnant women to inform a drug-associated risk for major birth defects and miscarriage. In animal reproduction studies, there was no embryo-fetal toxicity when oxycodone hydrochloride was orally administered to rats and rabbits, during the period of organogenesis, at doses 1.3 to 40 times the adult human dose of 60 mg/day, respectively. In a pre- and postnatal toxicity study, when oxycodone was orally administered to rats, there was transiently decreased pup body weight during lactation and the early post-weaning period at the dose equivalent to an adult dose of 60 mg/day. In several published studies, treatment of pregnant rats with oxycodone hydrochloride at clinically relevant doses and below resulted in neurobehavioral effects in offspring [see Data]. Based on animal data, advise pregnant women of the potential risk to a fetus.

The estimated background risk of major birth defects and miscarriage for the indicated population is unknown. All pregnancies have a background risk of birth defect, loss, or other adverse outcomes. In the U.S. general population, the estimated background risk of major birth defects and miscarriage in clinically recognized pregnancies is 2-4% and 15-20%, respectively.

Clinical Considerations

Fetal/Neonatal Adverse Reactions

Prolonged use of opioid analgesics during pregnancy for medical or nonmedical purposes can result in physical dependence in the neonate and neonatal opioid withdrawal syndrome shortly after birth.

Neonatal opioid withdrawal syndrome presents as irritability, hyperactivity and abnormal sleep pattern, high pitched cry, tremor, vomiting, diarrhea, and failure to gain weight. The onset, duration, and severity of neonatal opioid withdrawal syndrome vary based on the specific opioid used, duration of use, timing and amount of last maternal use, and rate of elimination of the drug by the newborn. Observe newborns for symptoms of neonatal opioid withdrawal syndrome and manage accordingly [see Warnings and Precautions (5.3)].

Labor or Delivery

Opioids cross the placenta and may produce respiratory depression and psycho-physiologic effects in neonates. An opioid antagonist, such as naloxone, must be available for reversal of opioid-induced respiratory depression in the neonate. OXYCODONE HCl EXTENDED-RELEASE TABLETS is not recommended for use in women immediately prior to labor, when use of shorter-acting analgesics or other analgesic techniques are more appropriate. Opioid analgesics, including OXYCODONE HCl EXTENDED-RELEASE TABLETS, can prolong labor through actions which temporarily reduce the strength, duration, and frequency of uterine contractions. However this effect is not consistent and may be offset by an increased rate of cervical dilatation, which tends to shorten labor. Monitor neonates exposed to opioid analgesics during labor for signs of excess sedation and respiratory depression.

Data

Animal Data

Pregnant rats were treated with 0.5, 2, 4, and 8 mg/kg oxycodone hydrochloride (0.08, 0.3, 0.7, and 1.3 times the human daily dose of 60 mg/day, respectively based on a mg/m2 basis) during the period of organogenesis. Oxycodone did not cause adverse effects to the fetus at exposures up to 1.3 times the human dose of 60 mg/day. The high dose produced maternal toxicity characterized by excessive gnawing on forelimbs and decreased body weight gain.

Pregnant rabbits were treated with 1, 5, 25, and 125 mg/kg oxycodone hydrochloride (0.3, 2, 8, and 40 times the human daily dose of 60 mg/day, respectively, based on a mg/m2 basis) during the period of organogenesis. Oxycodone did not cause adverse effects to the fetus at exposures up to 40 times the human dose of 60 mg/day. The 25 mg/kg and 125 mg/kg doses high doses produced maternal toxicity characterized by decreased food consumption and body weight gain.

Pregnant rats were treated with 0.5, 2, and 6 mg/kg oxycodone hydrochloride (0.08, 0.32, and 1 times the human daily dose of 60 mg/kg, respective, based on a mg/m2 basis, during the period of organogenesis through lactation. Decreased body weight was found during lactation and the early post-weaning phase in pups nursed by mothers given the highest dose used (6 mg/kg/day, equivalent to an adult human dose of 60 mg/day, on a mg/m2 basis). However, body weight of these pups recovered.

In published studies, offspring of pregnant rats administered oxycodone hydrochloride during gestation have been reported to exhibit neurobehavioral effects including altered stress responses and increased anxiety-like behavior (2 mg/kg/day IV from Gestation Day 8 to 21 and Postnatal Day 1, 3, and 5; 0.3 times an adult human oral dose of 60 mg/day on a mg/m2 basis), and altered learning and memory (15 mg/kg/day orally from breeding through parturition; 2.4 times an adult human oral dose of 60 mg/day on a mg/m2 basis).

8.2 Lactation

Oxycodone is present in breast milk. Published lactation studies report variable concentrations of oxycodone in breast milk with administration of immediate-release oxycodone to nursing mothers in the early postpartum period. The lactation studies did not assess breastfed infants for potential adverse reactions. Lactation studies have not been conducted with extended–release oxycodone, including OXYCODONE HCl EXTENDED-RELEASE TABLETS, and no information is available on the effects of the drug on the breastfed infant or the effects of the drug on milk production. Because of the potential for serious adverse reactions, including excess sedation and respiratory depression in a breastfed infant, advise patients that breastfeeding is not recommended during treatment with OXYCODONE HCl EXTENDED-RELEASE TABLETS.

Clinical Considerations

Infants exposed to OXYCODONE HCl EXTENDED-RELEASE TABLETS through breast milk should be monitored for excess sedation and respiratory depression. Withdrawal symptoms can occur in breast-fed infants when maternal administration of an opioid analgesic is stopped, or when breast-feeding is stopped.

8.3 Females and Males of Reproductive Potential

Infertility

Chronic use of opioids may cause reduced fertility in females and males of reproductive potential. It is not known whether these effects on fertility are reversible [see Adverse Reactions (6.2), Clinical Pharmacology (12.2)].

8.4 Pediatric Use

The safety and efficacy of OXYCODONE HCl EXTENDED-RELEASE TABLETS have been established in pediatric patients ages 11 to 16 years. Use of OXYCODONE HCl EXTENDED-RELEASE TABLETS is supported by evidence from adequate and well-controlled trials with OXYCODONE HCl EXTENDED-RELEASE TABLETS in adults as well as an open-label study in pediatric patients ages 6 to 16 years. However, there were insufficient numbers of patients less than 11 years of age enrolled in this study to establish the safety of the product in this age group.

The safety of OXYCODONE HCl EXTENDED-RELEASE TABLETS in pediatric patients was evaluated in 155 patients previously receiving and tolerating opioids for at least 5 consecutive days with a minimum of 20 mg per day of oxycodone or its equivalent on the two days immediately preceding dosing with OXYCODONE HCl EXTENDED-RELEASE TABLETS. Patients were started on a total daily dose ranging between 20 mg and 100 mg depending on prior opioid dose.

The most frequent adverse events observed in pediatric patients were vomiting, nausea, headache, pyrexia, and constipation [see Dosage and Administration (2.4), Adverse Reactions (6.1), Clinical Pharmacology (12.3) and Clinical Trials (14)].

8.5 Geriatric Use

In controlled pharmacokinetic studies in elderly subjects (greater than 65 years) the clearance of oxycodone was slightly reduced. Compared to young adults, the plasma concentrations of oxycodone were increased approximately 15% [see Clinical Pharmacology (12.3)]. Of the total number of subjects (445) in clinical studies of oxycodone hydrochloride controlled-release tablets, 148 (33.3%) were age 65 and older (including those age 75 and older) while 40 (9.0%) were age 75 and older. In clinical trials with appropriate initiation of therapy and dose titration, no untoward or unexpected adverse reactions were seen in the elderly patients who received oxycodone hydrochloride controlled-release tablets. Thus, the usual doses and dosing intervals may be appropriate for elderly patients. However, a dosage reduction in debilitated, non-opioid-tolerant patients is recommended [see Dosage and Administration (2.7)].

Respiratory depression is the chief risk for elderly patients treated with opioids, and has occurred after large initial doses were administered to patients who are not opioid-tolerant or when opioids were co-administered with other agents that depress respiration. Titrate the dosage of OXYCODONE HCl EXTENDED-RELEASE TABLETS slowly in these patients and monitor closely for signs of central nervous system and respiratory depression. [see Warnings and Precautions (5.6)].

Oxycodone is known to be substantially excreted by the kidney, and the risk of adverse reactions to this drug may be greater in patients with impaired renal function. Because elderly patients are more likely to have decreased renal function, care should be taken in dose selection, and it may be useful to monitor renal function.

8.6 Hepatic Impairment

A study of OXYCODONE HCl EXTENDED-RELEASE TABLETS in patients with hepatic impairment demonstrated greater plasma concentrations than those seen at equivalent doses in persons with normal hepatic function [see Clinical Pharmacology (12.3)]. Therefore, a dosage reduction is recommended for these patients [see Dosage and Administration (2.8)]. Monitor closely for signs of respiratory depression, sedation, and hypotension.

8.7 Renal Impairment

In patients with renal impairment, as evidenced by decreased creatinine clearance (<60 mL/min), the concentrations of oxycodone in the plasma are approximately 50% higher than in subjects with normal renal function [see Clinical Pharmacology (12.3)]. Follow a conservative approach to dose initiation and adjust according to the clinical situation.

8.8 Sex Differences

In pharmacokinetic studies with OXYCODONE HCl EXTENDED-RELEASE TABLETS, opioid-naïve females demonstrate up to 25% higher average plasma concentrations and greater frequency of typical opioid adverse events than males, even after adjustment for body weight. The clinical relevance of a difference of this magnitude is low for a drug intended for chronic usage at individualized dosages, and there was no male/female difference detected for efficacy or adverse events in clinical trials.

9 DRUG ABUSE AND DEPENDENCE

9.1 Controlled Substance

OXYCODONE HCl EXTENDED-RELEASE TABLETS contain oxycodone, a Schedule II controlled substance.

9.2 Abuse

OXYCODONE HCl EXTENDED-RELEASE TABLETS contains oxycodone, a substance with a high potential for abuse similar to other opioids including fentanyl, hydrocodone, hydromorphone, methadone, morphine, oxymorphone, and tapentadol. OXYCODONE HCl EXTENDED-RELEASE TABLETS can be abused and is subject to misuse, addiction, and criminal diversion [see Warnings and Precautions (5.1)].

The high drug content in extended-release formulations adds to the risk of adverse outcomes from abuse and misuse.

All patients treated with opioids require careful monitoring for signs of abuse and addiction, because use of opioid analgesic products carries the risk of addiction even under appropriate medical use.

Prescription drug abuse is the intentional non-therapeutic use of a prescription drug, even once, for its rewarding psychological or physiological effects. Drug addiction is a cluster of behavioral, cognitive, and physiological phenomena that develop after repeated substance use and includes: a strong desire to take the drug, difficulties in controlling its use, persisting in its use despite harmful consequences, a higher priority given to drug use than to other activities and obligations, increased tolerance, and sometimes a physical withdrawal.

"Drug-seeking" behavior is very common in persons with substance use disorders. Drug-seeking tactics include emergency calls or visits near the end of office hours, refusal to undergo appropriate examination, testing or referral, repeated “loss” of prescriptions, tampering with prescriptions, and reluctance to provide prior medical records or contact information for other treating healthcare provider(s). “Doctor shopping” (visiting multiple prescribers to obtain additional prescriptions) is common among drug abusers and people suffering from untreated addiction. Preoccupation with achieving adequate pain relief can be appropriate behavior in a patient with poor pain control.

Abuse and addiction are separate and distinct from physical dependence and tolerance. Healthcare providers should be aware that addiction may not be accompanied by concurrent tolerance and symptoms of physical dependence in all addicts. In addition, abuse of opioids can occur in the absence of true addiction.

OXYCODONE HCl EXTENDED-RELEASE TABLETS, like other opioids, can be diverted for non-medical use into illicit channels of distribution. Careful record-keeping of prescribing information, including quantity, frequency, and renewal requests, as required by state and federal law, is strongly advised.

Proper assessment of the patient, proper prescribing practices, periodic reevaluation of therapy, and proper dispensing and storage are appropriate measures that help to limit abuse of opioid drugs.

Risks Specific to Abuse of OXYCODONE HCl EXTENDED-RELEASE TABLETS

OXYCODONE HCl EXTENDED-RELEASE TABLETS are for oral use only. Abuse of OXYCODONE HCl EXTENDED-RELEASE TABLETS poses a risk of overdose and death. The risk is increased with concurrent use of OXYCODONE HCl EXTENDED-RELEASE TABLETS with alcohol and other central nervous system depressants. Taking cut, broken, chewed, crushed, or dissolved OXYCODONE HCl EXTENDED-RELEASE TABLETS enhances drug release and increases the risk of overdose and death.

With parenteral abuse, the inactive ingredients in OXYCODONE HCl EXTENDED-RELEASE TABLETS can be expected to result in local tissue necrosis, infection, pulmonary granulomas, and increased risk of endocarditis and valvular heart injury. Parenteral drug abuse is commonly associated with transmission of infectious diseases, such as hepatitis and HIV.

Abuse Deterrence Studies

OXYCODONE HCl EXTENDED-RELEASE TABLETS are formulated with inactive ingredients intended to make the tablet more difficult to manipulate for misuse and abuse. For the purposes of describing the results of studies of the abuse-deterrent characteristics of OXYCODONE HCl EXTENDED-RELEASE TABLETS resulting from a change in formulation, in this section, the original formulation of OXYCODONE HCl EXTENDED-RELEASE TABLETS, which is no longer marketed, will be referred to as “original OxyContin” and the reformulated, currently marketed product will be referred to as “OXYCODONE HCl EXTENDED-RELEASE TABLETS".

In Vitro Testing

In vitro physical and chemical tablet manipulation studies were performed to evaluate the success of different extraction methods in defeating the extended-release formulation. Results support that, relative to original OxyContin, there is an increase in the ability of OXYCODONE HCl EXTENDED-RELEASE TABLETS to resist crushing, breaking, and dissolution using a variety of tools and solvents. The results of these studies also support this finding for OXYCODONE HCl EXTENDED-RELEASE TABLETS relative to an immediate-release oxycodone. When subjected to an aqueous environment, OXYCODONE HCl EXTENDED-RELEASE TABLETS gradually forms a viscous hydrogel (i.e., a gelatinous mass) that resists passage through a needle.

Clinical Studies

In a randomized, double-blind, placebo-controlled 5-period crossover pharmacodynamic study, 30 recreational opioid users with a history of intranasal drug abuse received intranasally administered active and placebo drug treatments. The five treatment arms were finely crushed OXYCODONE HCl EXTENDED-RELEASE TABLETS 30 mg tablets, coarsely crushed OXYCODONE HCl EXTENDED-RELEASE TABLETS 30 mg tablets, finely crushed original OxyContin 30 mg tablets, powdered oxycodone HCl 30 mg, and placebo. Data for finely crushed OXYCODONE HCl EXTENDED-RELEASE TABLETS, finely crushed original OxyContin, and powdered oxycodone HCl are described below.

Drug liking was measured on a bipolar drug liking scale of 0 to 100 where 50 represents a neutral response of neither liking nor disliking, 0 represents maximum disliking and 100 represents maximum liking. Response to whether the subject would take the study drug again was also measured on a bipolar scale of 0 to 100 where 50 represents a neutral response, 0 represents the strongest negative response (“definitely would not take drug again”) and 100 represents the strongest positive response (“definitely would take drug again”).

Twenty-seven of the subjects completed the study. Incomplete dosing due to granules falling from the subjects’ nostrils occurred in 34% (n = 10) of subjects with finely crushed OXYCODONE HCl EXTENDED-RELEASE TABLETS, compared with 7% (n = 2) of subjects with finely crushed original OxyContin and no subjects with powdered oxycodone HCl.

The intranasal administration of finely crushed OXYCODONE HCl EXTENDED-RELEASE TABLETS was associated with a numerically lower mean and median drug liking score and a lower mean and median score for take drug again, compared to finely crushed original OxyContin or powdered oxycodone HCl as summarized in Table 5.

Table 5: Summary of Maximum Drug Liking (Emax) Data Following Intranasal Administration

*
Bipolar scales (0 = maximum negative response, 50 = neutral response, 100 = maximum positive response)

VAS Scale
(100 mm)*

OXYCODONE HCl EXTENDED-RELEASE TABLETS (finely crushed)

Original OxyContin (finely crushed)

Oxycodone HCl

(powdered)

Drug Liking

Mean (SE)

80.4 (3.9)

94.0 (2.7)

89.3 (3.1)

Median (Range)

88 (36-100)

100 (51-100)

100 (50-100)

Take Drug Again

Mean (SE)

64.0 (7.1)

89.6 (3.9)

86.6 (4.4)

Median (Range)

78 (0-100)

100 (20-100)

100 (0-100)

Figure 1 demonstrates a comparison of drug liking for finely crushed OXYCODONE HCl EXTENDED-RELEASE TABLETS compared to powdered oxycodone HCl in subjects who received both treatments. The Y-axis represents the percent of subjects attaining a percent reduction in drug liking for OXYCODONE HCl EXTENDED-RELEASE TABLETS vs. oxycodone HCl powder greater than or equal to the value on the X-axis. Approximately 44% (n = 12) had no reduction in liking with OXYCODONE HCl EXTENDED-RELEASE TABLETS relative to oxycodone HCl. Approximately 56% (n = 15) of subjects had some reduction in drug liking with OXYCODONE HCl EXTENDED-RELEASE TABLETS relative to oxycodone HCl. Thirty-three percent (n = 9) of subjects had a reduction of at least 30% in drug liking with OXYCODONE HCl EXTENDED-RELEASE TABLETS compared to oxycodone HCl, and approximately 22% (n = 6) of subjects had a reduction of at least 50% in drug liking with OXYCODONE HCl EXTENDED-RELEASE TABLETS compared to oxycodone HCl.

[Figure-1]

Figure 1: Percent Reduction Profiles for Emax of Drug Liking VAS for OXYCODONE HCl EXTENDED-RELEASE TABLETS vs. oxycodone HCl, N=27 Following Intranasal Administration

The results of a similar analysis of drug liking for finely crushed OXYCODONE HCl EXTENDED-RELEASE TABLETS relative to finely crushed original OxyContin were comparable to the results of finely crushed OXYCODONE HCl EXTENDED-RELEASE TABLETS relative to powdered oxycodone HCl. Approximately 43% (n = 12) of subjects had no reduction in liking with OXYCODONE HCl EXTENDED-RELEASE TABLETS relative to original OxyContin. Approximately 57% (n = 16) of subjects had some reduction in drug liking, 36% (n = 10) of subjects had a reduction of at least 30% in drug liking, and approximately 29% (n = 8) of subjects had a reduction of at least 50% in drug liking with OXYCODONE HCl EXTENDED-RELEASE TABLETS compared to original OxyContin.

Summary

The in vitro data demonstrate that OXYCODONE HCl EXTENDED-RELEASE TABLETS have physicochemical properties expected to make abuse via injection difficult. The data from the clinical study, along with support from the in vitro data, also indicate that OXYCODONE HCl EXTENDED-RELEASE TABLETS have physicochemical properties that are expected to reduce abuse via the intranasal route. However, abuse of OXYCODONE HCl EXTENDED-RELEASE TABLETS by these routes, as well as by the oral route, is still possible.

Additional data, including epidemiological data, when available, may provide further information on the impact of the current formulation of OXYCODONE HCl EXTENDED-RELEASE TABLETS on the abuse liability of the drug. Accordingly, this section may be updated in the future as appropriate.

OXYCODONE HCl EXTENDED-RELEASE TABLETS contain oxycodone, an opioid agonist and Schedule II controlled substance with an abuse liability similar to other opioid agonists, legal or illicit, including fentanyl, hydromorphone, methadone, morphine, and oxymorphone. OXYCODONE HCl EXTENDED-RELEASE TABLETS can be abused and is subject to misuse, addiction, and criminal diversion [see Warnings and Precautions (5.1) and Drug Abuse and Dependence (9.1)].

9.3 Dependence

Both tolerance and physical dependence can develop during chronic opioid therapy. Tolerance is the need for increasing doses of opioids to maintain a defined effect such as analgesia (in the absence of disease progression or other external factors). Tolerance may occur to both the desired and undesired effects of drugs, and may develop at different rates for different effects.

Physical dependence results in withdrawal symptoms after abrupt discontinuation or a significant dosage reduction of a drug. Withdrawal also may be precipitated through the administration of drugs with opioid antagonist activity (e.g., naloxone, nalmefene), mixed agonist/antagonist analgesics (e.g., pentazocine, butorphanol, nalbuphine), or partial agonists (e.g., buprenorphine). Physical dependence may not occur to a clinically significant degree until after several days to weeks of continued opioid usage.

OXYCODONE HCl EXTENDED-RELEASE TABLETS should not be abruptly discontinued [see Dosage and Administration (2.9)]. If OXYCODONE HCl EXTENDED-RELEASE TABLETS are abruptly discontinued in a physically-dependent patient, a withdrawal syndrome may occur. Some or all of the following can characterize this syndrome: restlessness, lacrimation, rhinorrhea, yawning, perspiration, chills, myalgia, and mydriasis. Other signs and symptoms also may develop, including irritability, anxiety, backache, joint pain, weakness, abdominal cramps, insomnia, nausea, anorexia, vomiting, diarrhea, or increased blood pressure, respiratory rate, or heart rate.

Infants born to mothers physically dependent on opioids will also be physically dependent and may exhibit respiratory difficulties and withdrawal signs [see Use in Specific Populations (8.1)].

10 OVERDOSAGE

Clinical Presentation

Acute overdose with OXYCODONE HCl EXTENDED-RELEASE TABLETS can be manifested by respiratory depression, somnolence progressing to stupor or coma, skeletal muscle flaccidity, cold and clammy skin, constricted pupils, and in some cases, pulmonary edema, bradycardia, hypotension, partial or complete airway obstruction, atypical snoring, and death. Marked mydriasis rather than miosis may be seen with hypoxia in overdose situations.

Treatment of Overdose

In case of overdose, priorities are the reestablishment of a patent and protected airway and institution of assisted or controlled ventilation, if needed. Employ other supportive measures (including oxygen, vasopressors) in the management of circulatory shock and pulmonary edema as indicated. Cardiac arrest or arrhythmias will require advanced life support techniques.

The opioid antagonists, naloxone or nalmefene, are specific antidotes to respiratory depression resulting from opioid overdose. For clinically significant respiratory or circulatory depression secondary to oxycodone overdose, administer an opioid antagonist. Opioid antagonists should not be administered in the absence of clinically significant respiratory or circulatory depression secondary to oxycodone overdose.

Because the duration of reversal is expected to be less than the duration of action of oxycodone in OXYCODONE HCl EXTENDED-RELEASE TABLETS, carefully monitor the patient until spontaneous respiration is reliably reestablished. OXYCODONE HCl EXTENDED-RELEASE TABLETS will continue to release oxycodone and add to the oxycodone load for 24 to 48 hours or longer following ingestion, necessitating prolonged monitoring. If the response to an opioid antagonist is suboptimal or only brief in nature, administer additional antagonist as directed by the product’s prescribing information.

In an individual physically dependent on opioids, administration of the recommended usual dosage of the antagonist will precipitate an acute withdrawal syndrome. The severity of the withdrawal symptoms experienced will depend on the degree of physical dependence and the dose of the antagonist administered. If a decision is made to treat serious respiratory depression in the physically dependent patient, administration of the antagonist should be initiated with care and by titration with smaller than usual doses of the antagonist.

11 DESCRIPTION

OXYCODONE HCl EXTENDED-RELEASE TABLETS are an opioid agonist supplied in 10 mg, 20 mg, 40 mg, and 80 mg tablets for oral administration. The tablet strengths describe the amount of oxycodone per tablet as the hydrochloride salt. The structural formula for oxycodone hydrochloride is as follows:

[chemical-structure]

C 18 H 21 NO 4 • HCl MW 351.83

The chemical name is 4, 5α-epoxy-14-hydroxy-3-methoxy-17-methylmorphinan-6-one hydrochloride.

Oxycodone is a white, odorless crystalline powder derived from the opium alkaloid, thebaine. Oxycodone hydrochloride dissolves in water (1 g in 6 to 7 mL). It is slightly soluble in alcohol (octanol water partition coefficient 0.7).

The 10 mg, 20 mg, 40 mg, and 80 mg tablets contain the following inactive ingredients: butylated hydroxytoluene (BHT), hypromellose, polyethylene glycol 400, polyethylene oxide, magnesium stearate, titanium dioxide.

The 10 mg tablets also contain hydroxypropyl cellulose.

The 20 mg tablets also contain polysorbate 80 and red iron oxide.

The 40 mg tablets also contain polysorbate 80 and yellow iron oxide.

The 80 mg tablets also contain hydroxypropyl cellulose, yellow iron oxide and FD&C Blue #2/Indigo Carmine Aluminum Lake.

12 CLINICAL PHARMACOLOGY

12.1 Mechanism of Action

Oxycodone is a full opioid agonist and is relatively selective for the mu receptor, although it can bind to other opioid receptors at higher doses. The principal therapeutic action of oxycodone is analgesia. Like all full opioid agonists, there is no ceiling effect to analgesia for oxycodone. Clinically, dosage is titrated to provide adequate analgesia and may be limited by adverse reactions, including respiratory and CNS depression.

The precise mechanism of the analgesic action is unknown. However, specific CNS opioid receptors for endogenous compounds with opioid-like activity have been identified throughout the brain and spinal cord and are thought to play a role in the analgesic effects of this drug.

12.2 Pharmacodynamics

Effects on the Central Nervous System

Oxycodone produces respiratory depression by direct action on brain stem respiratory centers. The respiratory depression involves a reduction in the responsiveness of the brain stem respiratory centers to both increases in CO2 tension and electrical stimulation.

Oxycodone causes miosis, even in total darkness. Pinpoint pupils are a sign of opioid overdose but are not pathognomonic (e.g., pontine lesions of hemorrhagic or ischemic origin may produce similar findings). Marked mydriasis rather than miosis may be seen with hypoxia in overdose situations [see Overdosage (10)].

Effects on the Gastrointestinal Tract and Other Smooth Muscle

Oxycodone causes a reduction in motility associated with an increase in smooth muscle tone in the antrum of the stomach and duodenum. Digestion of food in the small intestine is delayed and propulsive contractions are decreased. Propulsive peristaltic waves in the colon are decreased, while tone may be increased to the point of spasm, resulting in constipation. Other opioid-induced effects may include a reduction in biliary and pancreatic secretions, spasm of sphincter of Oddi, and transient elevations in serum amylase.

Effects on the Cardiovascular System

Oxycodone produces peripheral vasodilation which may result in orthostatic hypotension or syncope. Manifestations of histamine release and/or peripheral vasodilation may include pruritus, flushing, red eyes, sweating, and/or orthostatic hypotension.

Effects on the Endocrine System

Opioids inhibit the secretion of adrenocorticotropic hormone (ACTH), cortisol, and luteinizing hormone (LH) in humans [see Adverse Reactions (6.2)]. They also stimulate prolactin, growth hormone (GH) secretion, and pancreatic secretion of insulin and glucagon.

Chronic use of opioids may influence the hypothalamic-pituitary-gonadal axis, leading to androgen deficiency that may manifest as low libido, impotence, erectile dysfunction, amenorrhea, or infertility. The causal role of opioids in the clinical syndrome of hypogonadism is unknown because the various medical, physical, lifestyle, and psychological stressors that may influence gonadal hormone levels have not been adequately controlled for in studies conducted to date [see Adverse Reactions (6.2)].

Effects on the Immune System

Opioids have been shown to have a variety of effects on components of the immune system in in vitro and animal models. The clinical significance of these findings is unknown. Overall, the effects of opioids appear to be modestly immunosuppressive.

Concentration –Efficacy Relationships

Studies in normal volunteers and patients reveal predictable relationships between oxycodone dosage and plasma oxycodone concentrations, as well as between concentration and certain expected opioid effects, such as pupillary constriction, sedation, overall subjective “drug effect”, analgesia and feelings of relaxation.

The minimum effective analgesic concentration will vary widely among patients, especially among patients who have been previously treated with potent agonist opioids. The minimum effective analgesic concentration of oxycodone for any individual patient may increase over time due to an increase in pain, the development of a new pain syndrome, and/or the development of analgesic tolerance [see Dosage and Administration (2.1, 2.5)].

Concentration –Adverse Reaction Relationships

There is a relationship between increasing oxycodone plasma concentration and increasing frequency of dose-related opioid adverse reactions such as nausea, vomiting, CNS effects, and respiratory depression. In opioid-tolerant patients, the situation may be altered by the development of tolerance to opioid-related adverse reactions [see Dosage and Administration (2.1, 2.5)].

12.3 Pharmacokinetics

The activity of OXYCODONE HCl EXTENDED-RELEASE TABLETS is primarily due to the parent drug oxycodone. OXYCODONE HCl EXTENDED-RELEASE TABLETS are designed to provide delivery of oxycodone over 12 hours.

Cutting, breaking, chewing, crushing or dissolving OXYCODONE HCl EXTENDED-RELEASE TABLETS impairs the controlled-release delivery mechanism and results in the rapid release and absorption of a potentially fatal dose of oxycodone.

Oxycodone release from OXYCODONE HCl EXTENDED-RELEASE TABLETS is pH independent. The oral bioavailability of oxycodone is 60% to 87%. The relative oral bioavailability of oxycodone from OXYCODONE HCl EXTENDED-RELEASE TABLETS to that from immediate-release oral dosage forms is 100%. Upon repeated dosing with OXYCODONE HCl EXTENDED-RELEASE TABLETS in healthy subjects in pharmacokinetic studies, steady-state levels were achieved within 24-36 hours. Oxycodone is extensively metabolized and eliminated primarily in the urine as both conjugated and unconjugated metabolites. The apparent elimination half-life (t½) of oxycodone following the administration of OXYCODONE HCl EXTENDED-RELEASE TABLETS was 4.5 hours compared to 3.2 hours for immediate-release oxycodone.

Absorption

About 60% to 87% of an oral dose of oxycodone reaches the central compartment in comparison to a parenteral dose. This high oral bioavailability is due to low pre-systemic and/or first-pass metabolism.

Plasma Oxycodone Concentration over Time

Dose proportionality has been established for OXYCODONE HCl EXTENDED-RELEASE TABLETS 10 mg, 20 mg, 40 mg, and 80 mg tablet strengths for both peak plasma concentrations (Cmax) and extent of absorption (AUC) (see TABLE 6). Given the short elimination t½ of oxycodone, steady-state plasma concentrations of oxycodone are achieved within 24-36 hours of initiation of dosing with OXYCODONE HCl EXTENDED-RELEASE TABLETS. In a study comparing 10 mg of OXYCODONE HCl EXTENDED-RELEASE TABLETS every 12 hours to 5 mg of immediate-release oxycodone every 6 hours, the two treatments were found to be equivalent for AUC and Cmax, and similar for Cmin (trough) concentrations.

Table 6: Mean [% coefficient of variation]

*
for single-dose AUC = AUC 0-inf
†
data obtained while subjects received naltrexone, which can enhance absorption

Regimen

Dosage Form

AUC (ng•hr/mL)*

Cmax
(ng/mL)

Tmax

(hr)

Single Dose†

10 mg

136 [27]

11.5 [27]

5.11 [21]

20 mg

248 [25]

22.7 [25]

4.63 [22]

40 mg

497 [27]

47.4 [30]

4.40 [22]

80 mg

908 [21]

87.1 [29]

4.27 [26]

Food Effects

Food has no significant effect on the extent of absorption of oxycodone from OXYCODONE HCl EXTENDED-RELEASE TABLETS.

Distribution

Following intravenous administration, the steady-state volume of distribution (Vss) for oxycodone was 2.6 L/kg. Oxycodone binding to plasma protein at 37°C and a pH of 7.4 was about 45%. Once absorbed, oxycodone is distributed to skeletal muscle, liver, intestinal tract, lungs, spleen, and brain. Oxycodone has been found in breast milk [see Use in Specific Populations (8.4)].

Elimination

Metabolism

Oxycodone is extensively metabolized by multiple metabolic pathways to produce noroxycodone, oxymorphone and noroxymorphone, which are subsequently glucuronidated. Noroxycodone and noroxymorphone are the major circulating metabolites. CYP3A mediated N-demethylation to noroxycodone is the primary metabolic pathway of oxycodone with a lower contribution from CYP2D6 mediated O-demethylation to oxymorphone. Therefore, the formation of these and related metabolites can, in theory, be affected by other drugs [see Drug Interactions (7)].

Noroxycodone exhibits very weak anti-nociceptive potency compared to oxycodone, however, it undergoes further oxidation to produce noroxymorphone, which is active at opioid receptors. Although noroxymorphone is an active metabolite and present at relatively high concentrations in circulation, it does not appear to cross the blood-brain barrier to a significant extent. Oxymorphone is present in the plasma only at low concentrations and undergoes further metabolism to form its glucuronide and noroxymorphone. Oxymorphone has been shown to be active and possessing analgesic activity but its contribution to analgesia following oxycodone administration is thought to be clinically insignificant. Other metabolites (α- and ß-oxycodol, noroxycodol and oxymorphol) may be present at very low concentrations and demonstrate limited penetration into the brain as compared to oxycodone. The enzymes responsible for keto-reduction and glucuronidation pathways in oxycodone metabolism have not been established.

Excretion

Oxycodone and its metabolites are excreted primarily via the kidney. The amounts measured in the urine have been reported as follows: free and conjugated oxycodone 8.9%, free noroxycodone 23%, free oxymorphone less than 1%, conjugated oxymorphone 10%, free and conjugated noroxymorphone 14%, reduced free and conjugated metabolites up to 18%. The total plasma clearance was approximately 1.4 L/min in adults.

Specific Populations

Age: Geriatric Population

The plasma concentrations of oxycodone are only nominally affected by age, being 15% greater in elderly as compared to young subjects (age 21-45).

Age: Pediatric Population

In the pediatric age group of 11 years of age and older, systemic exposure of oxycodone is expected to be similar to adults at any given dose of OXYCODONE HCl EXTENDED-RELEASE TABLETS.

Sex

Across individual pharmacokinetic studies, average plasma oxycodone concentrations for female subjects were up to 25% higher than for male subjects on a body weight-adjusted basis. The reason for this difference is unknown [see Use in Specific Populations (8.9)].

Hepatic Impairment

Data from a study involving 24 patients with mild to moderate hepatic dysfunction show peak plasma oxycodone and noroxycodone concentrations 50% and 20% higher, respectively, than healthy subjects. AUC values are 95% and 65% higher, respectively. Oxymorphone peak plasma concentrations and AUC values are lower by 30% and 40%. These differences are accompanied by increases in some, but not other, drug effects. The mean elimination t½ for oxycodone increased by 2.3 hours.

Renal Impairment

Data from a pharmacokinetic study involving 13 patients with mild to severe renal dysfunction (creatinine clearance <60 mL/min) showed peak plasma oxycodone and noroxycodone concentrations 50% and 20% higher, respectively, and AUC values for oxycodone, noroxycodone, and oxymorphone 60%, 50%, and 40% higher than normal subjects, respectively. This was accompanied by an increase in sedation but not by differences in respiratory rate, pupillary constriction, or several other measures of drug effect. There was an increase in mean elimination t½ for oxycodone of 1 hour.

Drug Interaction Studies

CYP3A4 Inhibitors

CYP3A4 is the major isoenzyme involved in noroxycodone formation. Co-administration of OXYCODONE HCl EXTENDED-RELEASE TABLETS (10 mg single dose) and the CYP3A4 inhibitor ketoconazole (200 mg BID) increased oxycodone AUC and Cmax by 170% and 100%, respectively [see Drug Interactions (7)].

CYP3A4 Inducers

A published study showed that the co-administration of rifampin, a drug metabolizing enzyme inducer, decreased oxycodone AUC and Cmax values by 86% and 63%, respectively [see Drug Interactions (7)].

CYP2D6 Inhibitors

Oxycodone is metabolized in part to oxymorphone via CYP2D6. While this pathway may be blocked by a variety of drugs such as certain cardiovascular drugs (e.g., quinidine) and antidepressants (e.g., fluoxetine), such blockade has not been shown to be of clinical significance with OXYCODONE HCl EXTENDED-RELEASE TABLETS [see Drug Interactions (7)].

13 NONCLINICAL TOXICOLOGY

13.1 Carcinogenesis, Mutagenesis, Impairment of Fertility

Carcinogenesis

Long-term studies in animals to evaluate the carcinogenic potential of oxycodone have not been conducted.

Mutagenesis

Oxycodone was genotoxic in the in vitro mouse lymphoma assay. Oxycodone was negative when tested at appropriate concentrations in the in vitro chromosomal aberration assay, the in vitro bacterial reverse mutation assay (Ames test), and the in vivo bone marrow micronucleus assay in mice.

Impairment of Fertility

In a study of reproductive performance, rats were administered a once daily gavage dose of the vehicle or oxycodone hydrochloride (0.5, 2, and 8 mg/kg/day). Male rats were dosed for 28 days before cohabitation with females, during the cohabitation and until necropsy (2-3 weeks post-cohabitation). Females were dosed for 14 days before cohabitation with males, during cohabitation and up to Gestation Day 6. Oxycodone hydrochloride did not affect reproductive function in male or female rats at any dose tested (up to 8 mg/kg/day), up to 1.3 times a human dose of 60 mg/day.

14 CLINICAL STUDIES

Adult Clinical Study

A double-blind, placebo-controlled, fixed-dose, parallel group, two-week study was conducted in 133 patients with persistent, moderate to severe pain, who were judged as having inadequate pain control with their current therapy. In this study, OXYCODONE HCl EXTENDED-RELEASE TABLETS 20 mg, but not 10 mg, was statistically significant in pain reduction compared with placebo.

Pediatric Clinical Study

OXYCODONE HCl EXTENDED-RELEASE TABLETS has been evaluated in an open-label clinical trial of 155 opioid-tolerant pediatric patients with moderate to severe chronic pain. The mean duration of therapy was 20.7 days (range 1 to 43 days). The starting total daily doses ranged from 20 mg to 100 mg based on the patient’s prior opioid dose. The mean daily dose was 33.30 mg (range 20 to 140 mg/day). In an extension study, 23 of the 155 patients were treated beyond four weeks, including 13 for 28 weeks. Too few patients less than 11 years were enrolled in the clinical trial to provide meaningful safety data in this age group.

16 HOW SUPPLIED/STORAGE AND HANDLING

OXYCODONE HCl EXTENDED-RELEASE TABLETS 10 mg are film-coated, round, white-colored, bi-convex tablets debossed with OP on one side and 10 on the other and are supplied as child-resistant closure, opaque plastic bottles of 100 (NDC 0093-5731-01).

OXYCODONE HCl EXTENDED-RELEASE TABLETS 20 mg are film-coated, round, pink-colored, bi-convex tablets debossed with OP on one side and 20 on the other and are supplied as child-resistant closure, opaque plastic bottles of 100 (NDC 0093-5732-01).

OXYCODONE HCl EXTENDED-RELEASE TABLETS 40 mg are film-coated, round, yellow-colored, bi-convex tablets debossed with OP on one side and 40 on the other and are supplied as child-resistant closure, opaque plastic bottles of 100 (NDC 0093-5733-01).

OXYCODONE HCl EXTENDED-RELEASE TABLETS 80 mg are film-coated, round, green-colored, bi-convex tablets debossed with OP on one side and 80 on the other and are supplied as child-resistant closure, opaque plastic bottles of 100 (NDC 0093-5734-01).

Store at 25°C (77°F); excursions permitted between 15°-30°C (59°-86°F) [see USP Controlled Room Temperature].

Dispense in tight, light-resistant container.

17 PATIENT COUNSELING INFORMATION

Advise the patient to read the FDA-approved patient labeling (Medication Guide).

Addiction, Abuse and Misuse

Inform patients that the use of OXYCODONE HCl EXTENDED-RELEASE TABLETS, even when taken as recommended, can result in addiction, abuse, and misuse, which can lead to overdose and death [see Warnings and Precautions (5.1)]. Instruct patients not to share OXYCODONE HCl EXTENDED-RELEASE TABLETS with others and to take steps to protect OXYCODONE HCl EXTENDED-RELEASE TABLETS from theft or misuse.

Life-Threatening Respiratory Depression

Inform patients of the risk of life-threatening respiratory depression, including information that the risk is greatest when starting OXYCODONE HCl EXTENDED-RELEASE TABLETS or when the dosage is increased, and that it can occur even at recommended dosages [see Warnings and Precautions (5.2)].Advise patients how to recognize respiratory depression and to seek medical attention if breathing difficulties develop.

To guard against excessive exposure to OXYCODONE HCl EXTENDED-RELEASE TABLETS by young children, advise caregivers to strictly adhere to recommended OXYCODONE HCl EXTENDED-RELEASE TABLETS dosing.

Accidental Ingestion

Inform patients that accidental ingestion, especially by children, may result in respiratory depression or death [see Warnings and Precautions (5.2)]. Instruct patients to take steps to store OXYCODONE HCl EXTENDED-RELEASE TABLETS securely and to dispose of unused OXYCODONE HCl EXTENDED-RELEASE TABLETS by flushing the tablets down the toilet.

Interactions with Benzodiazepines or Other CNS Depressants

Inform patients and caregivers that potentially fatal additive effects may occur if OXYCODONE HCl EXTENDED-RELEASE TABLETS are used with benzodiazepines or other CNS depressants, including alcohol, and not to use these concomitantly unless supervised by a healthcare provider [see Warnings and Precautions (5.5), Drug Interactions (7)].

Serotonin Syndrome

Inform patients that opioids could cause a rare but potentially life-threatening condition resulting from concomitant administration of serotonergic drugs. Warn patients of the symptoms of serotonin syndrome and to seek medical attention right away if symptoms develop. Instruct patients to inform their healthcare provider if they are taking, or plan to take serotonergic medications [see Drug Interactions (7)].

MAOI Interaction

Inform patients to avoid taking OXYCODONE HCl EXTENDED-RELEASE TABLETS while using any drugs that inhibit monoamine oxidase. Patients should not start MAOIs while taking OXYCODONE HCl EXTENDED-RELEASE TABLETS [see Drug Interactions (7)].

Adrenal Insufficiency

Inform patients that opioids could cause adrenal insufficiency, a potentially life-threatening condition. Adrenal insufficiency may present with non-specific symptoms and signs such as nausea, vomiting, anorexia, fatigue, weakness, dizziness, and low blood pressure. Advise patients to seek medical attention if they experience a constellation of these symptoms [see Warnings and Precautions (5.7)].

Important Administration Instructions

Instruct patients how to properly take OXYCODONE HCl EXTENDED-RELEASE TABLETS, including the following:

•
OXYCODONE HCl EXTENDED-RELEASE TABLETS are designed to work properly only if swallowed intact. Taking cut, broken, chewed, crushed, or dissolved OXYCODONE HCl EXTENDED-RELEASE TABLETS can result in a fatal overdose [see Dosage and Administration (2.1)].
•
OXYCODONE HCl EXTENDED-RELEASE TABLETS should be taken one tablet at a time [see Dosage and Administration (2.1)].
•
Do not pre-soak, lick, or otherwise wet the tablet prior to placing in the mouth [see Dosage and Administration (2.1)].
•
Take each tablet with enough water to ensure complete swallowing immediately after placing in the mouth [see Dosage and Administration (2.1)].
•
Do not discontinue OXYCODONE HCl EXTENDED-RELEASE TABLETS without first discussing the need for a tapering regimen with the prescriber [see Dosage and Administration (2.9)].

Hypotension

Inform patients that OXYCODONE HCl EXTENDED-RELEASE TABLETS may cause orthostatic hypotension and syncope. Instruct patients how to recognize symptoms of low blood pressure and how to reduce the risk of serious consequences should hypotension occur (e.g., sit or lie down, carefully rise from a sitting or lying position) [see Warnings and Precautions (5.8)].

Anaphylaxis

Inform patients that anaphylaxis has been reported with ingredients contained in OXYCODONE HCl EXTENDED-RELEASE TABLETS. Advise patients how to recognize such a reaction and when to seek medical attention [see Contraindications (4), Adverse Reactions (6)].

Pregnancy

Neonatal Opioid Withdrawal Syndrome

Inform female patients of reproductive potential that prolonged use of OXYCODONE HCl EXTENDED-RELEASE TABLETS during pregnancy can result in neonatal opioid withdrawal syndrome, which may be life-threatening if not recognized and treated [see Warnings and Precautions (5.3), Use in Specific Populations (8.1)].

Embryo-Fetal Toxicity

Inform female patients of reproductive potential that OXYCODONE HCl EXTENDED-RELEASE TABLETS can cause fetal harm and to inform their healthcare provider of a known or suspected pregnancy [see Use in Specific Populations (8.1)].

Lactation:

Advise patients that breastfeeding is not recommended during treatment with OXYCODONE HCl EXTENDED-RELEASE TABLETS [see Use in Specific Populations (8.2)]

Infertility

Inform patients that chronic use of opioids may cause reduced fertility. It is not known whether these effects on fertility are reversible [see Use in Specific Populations (8.3)].

Driving or Operating Heavy Machinery

Inform patients that OXYCODONE HCl EXTENDED-RELEASE TABLETS may impair the ability to perform potentially hazardous activities such as driving a car or operating heavy machinery. Advise patients not to perform such tasks until they know how they will react to the medication [see Warnings and Precautions (5.14)].

Constipation

Advise patients of the potential for severe constipation, including management instructions and when to seek medical attention [see Adverse Reactions (6)].

Disposal of Unused OXYCODONE HCl EXTENDED-RELEASE TABLETS

Advise patients to flush the unused tablets down the toilet when OXYCODONE HCl EXTENDED-RELEASE TABLETS are no longer needed.

Healthcare professionals can telephone 1-888-838-2872 for information on this product.

Manufactured by:

Purdue Pharmaceuticals L.P.

Wilson, NC 27893

Distributed by:

Teva Pharmaceuticals USA, Inc.

North Wales, PA 19454

U.S. Patent Numbers 6,488,963; 7,129,248; 8,309,060; 8,808,741; 8,821,929; 8,894,987; 8,894,988; 9,060,976; 9,073,933; 9,492,389, 9,492,391, 9,492,392, 9,492,393, and 9,522,919

MEDICATION GUIDE

OXYCODONE (OX-ee-KOH-dohn) HCl EXTENDED-RELEASE TABLETS , CII

OXYCODONE HCl EXTENDED-RELEASE TABLETS are:

•
A strong prescription pain medicine that contains an opioid (narcotic) that is used to manage pain severe enough to require daily around-the-clock, long-term treatment with an opioid, when other pain treatments such as non-opioid pain medicines or immediate-release opioid medicines do not treat your pain well enough or you cannot tolerate them.
•
A long-acting (extended-release) opioid pain medicine that can put you at risk for overdose and death. Even if you take your dose correctly as prescribed you are at risk for opioid addiction, abuse, and misuse that can lead to death.
•
Not for use to treat pain that is not around-the-clock.
•
Not for use in children less than 11 years of age and who are not already using opioid pain medicines regularly to manage pain severe enough to require daily around-the-clock long-term treatment of pain with an opioid

Important information about OXYCODONE HCl EXTENDED-RELEASE TABLETS:

•
Get emergency help right away if you take too much OXYCODONE HCl EXTENDED-RELEASE TABLETS (overdose). When you first start taking OXYCODONE HCl EXTENDED-RELEASE TABLETS, when your dose is changed, or if you take too much (overdose), serious or life-threatening breathing problems that can lead to death may occur.
•
Taking OXYCODONE HCl EXTENDED-RELEASE TABLETS with other opioid medicines, benzodiazepines, alcohol, or other central nervous system depressants (including street drugs) can cause severe drowsiness, decreased awareness, breathing problems, coma, and death.
•
Never give anyone else your OXYCODONE HCl EXTENDED-RELEASE TABLETS. They could die from taking it. Store OXYCODONE HCl EXTENDED-RELEASE TABLETS away from children and in a safe place to prevent stealing or abuse. Selling or giving away OXYCODONE HCl EXTENDED-RELEASE TABLETS is against the law.

Do not take OXYCODONE HCl EXTENDED-RELEASE TABLETS if you have:

•
severe asthma, trouble breathing, or other lung problems
•
a bowel blockage or have narrowing of the stomach or intestines.

Before taking OXYCODONE HCl EXTENDED-RELEASE TABLETS, tell your healthcare provider if you have a history of:

•
head injury, seizures
•
liver, kidney, thyroid problems
•
problems urinating
•
pancreas or gallbladder problems
•
abuse of street or prescription drugs, alcohol addiction, or mental health problems.

Tell your healthcare provider if you are:

•
pregnant or planning to become pregnant. Prolonged use of OXYCODONE HCl EXTENDED-RELEASE TABLETS during pregnancy can cause withdrawal symptoms in your newborn baby that could be life-threatening if not recognized and treated.
•
breastfeeding. Not recommended during treatment with OXYCODONE HCl EXTENDED-RELEASE TABLETS. It may harm your baby.
•
taking prescription or over-the-counter medicines, vitamins, or herbal supplements. TakingOXYCODONE HCl EXTENDED-RELEASE TABLETS with certain other medicines can cause serious side effects that could lead to death.

When takingOXYCODONE HCl EXTENDED-RELEASE TABLETS:

•
Do not change your dose. Take OXYCODONE HCl EXTENDED-RELEASE TABLETS exactly as prescribed by your healthcare provider. Use the lowest dose possible for the shortest time needed.
•
Take your prescribed dose every 12 hours at the same time every day. Do not take more than your prescribed dose in 12 hours. If you miss a dose, take your next dose at your usual time.
•
Swallow OXYCODONE HCl EXTENDED-RELEASE TABLETS whole. Do not cut, break, chew, crush, dissolve, snort, or inject OXYCODONE HCl EXTENDED-RELEASE TABLETS because this may cause you to overdose and die.
•
OXYCODONE HCl EXTENDED-RELEASE TABLETS should be taken 1 tablet at a time. Do not pre-soak, lick, or wet the tablet before placing in your mouth to avoid choking on the tablet.
•
Call your healthcare provider if the dose you are taking does not control your pain.
•
Do not stop taking OXYCODONE HCl EXTENDED-RELEASE TABLETS without talking to your healthcare provider.
•
After you stop taking OXYCODONE HCl EXTENDED-RELEASE TABLETS, flush any unused tablets down the toilet.

While taking OXYCODONE HCl EXTENDED-RELEASE TABLETS DO NOT:

•
Drive or operate heavy machinery until you know how OXYCODONE HCl EXTENDED-RELEASE TABLETS affects you. OXYCODONE HCl EXTENDED-RELEASE TABLETS can make you sleepy, dizzy, or lightheaded.
•
Drink alcohol, or use prescription or over-the-counter medicines that contain alcohol. Using products containing alcohol during treatment with OXYCODONE HCl EXTENDED-RELEASE TABLETS may cause you to overdose and die.

The possible side effects of OXYCODONE HCl EXTENDED-RELEASE TABLETS are:

•
constipation, nausea, sleepiness, vomiting, tiredness, headache, dizziness, abdominal pain. Call your healthcare provider if you have any of these symptoms and they are severe.

Get emergency medical help if you have: trouble breathing, shortness of breath, fast heartbeat, chest pain, swelling of your face, tongue, or throat, extreme drowsiness, light-headedness when changing positions, feeling faint, agitation, high body temperature, trouble walking, stiff muscles, or mental changes such as confusion.

These are not all the possible side effects of OXYCODONE HCl EXTENDED-RELEASE TABLETS. Call your doctor for medical advice about side effects.

You may report side effects to FDA at 1-800-FDA-1088. For more information go to dailymed.nlm.nih.gov

Distributed by: Teva Pharmaceuticals USA, Inc.,North Wales, PA 19454

This Medication Guide has been approved by the U.S. Food and Drug Administration.

Revised: 12/2016